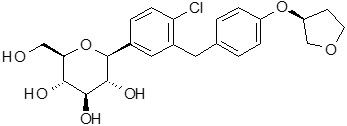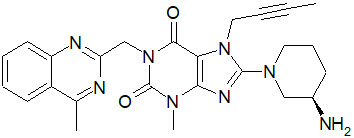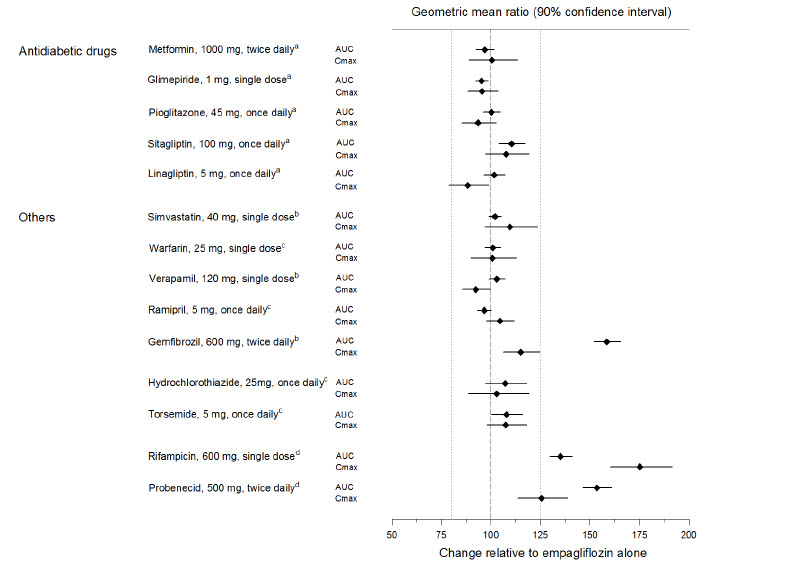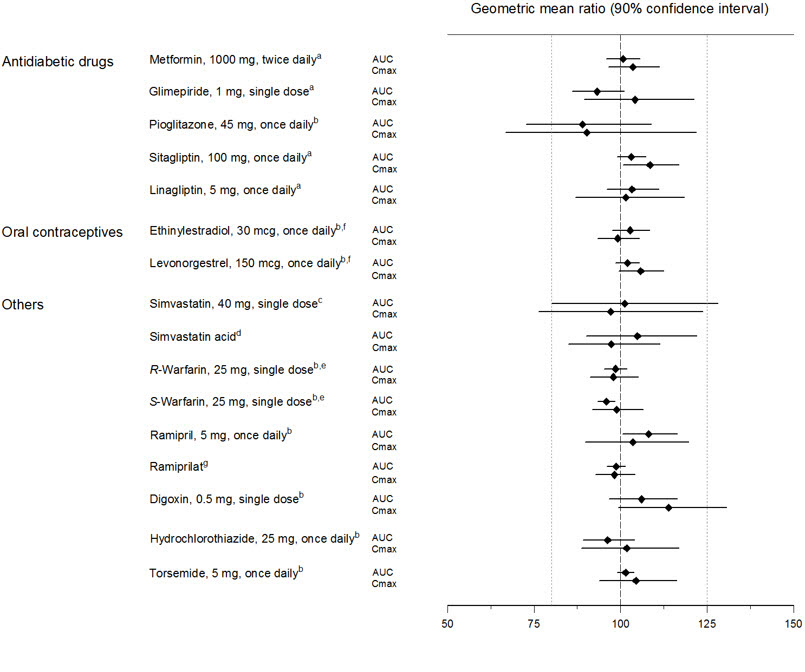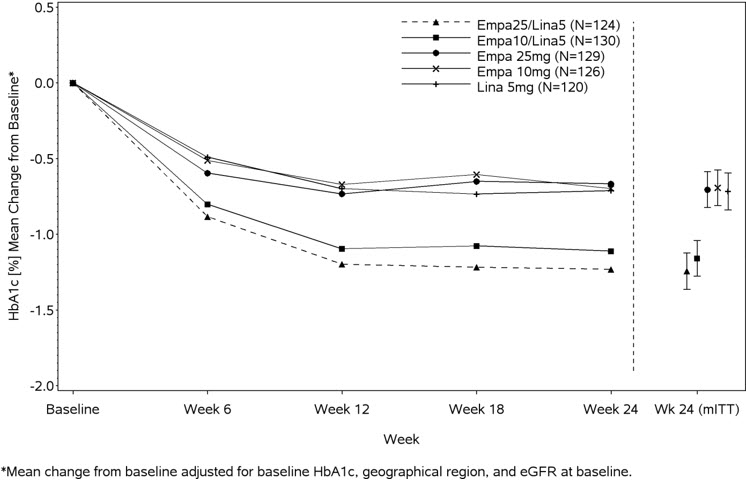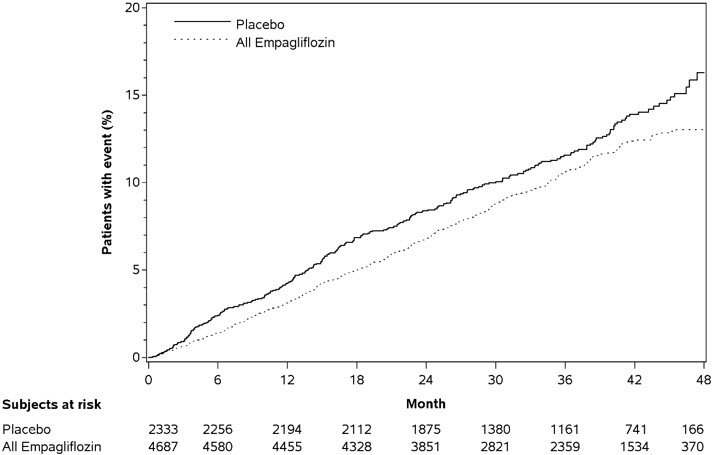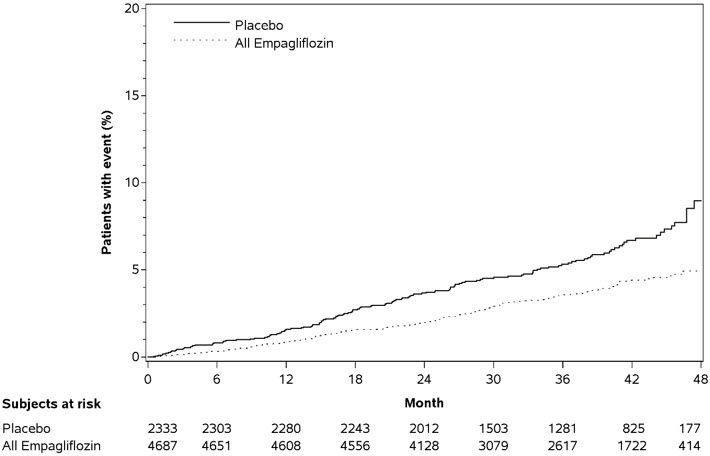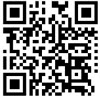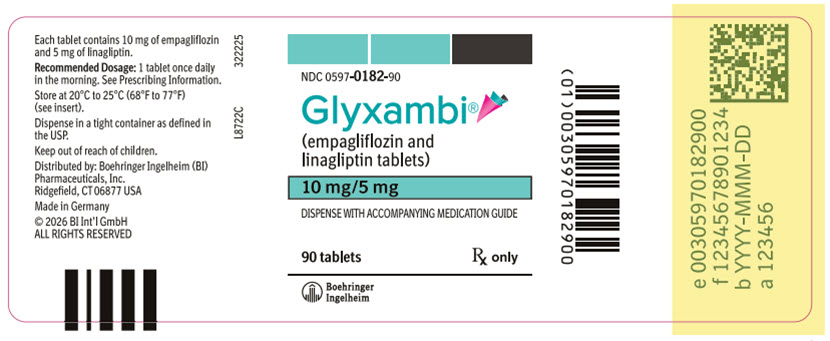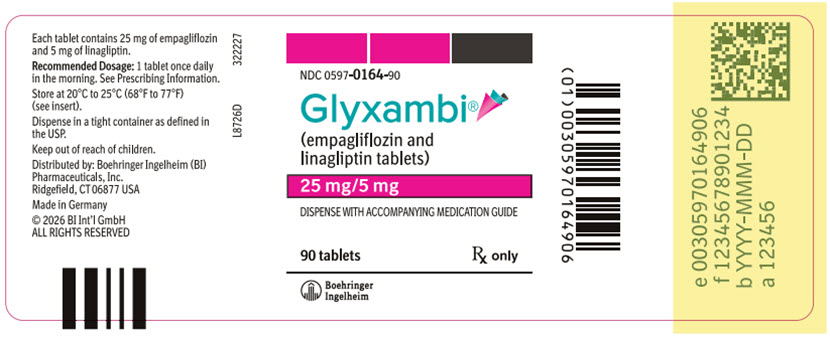 DRUG LABEL: Glyxambi
NDC: 0597-0182 | Form: TABLET, FILM COATED
Manufacturer: Boehringer Ingelheim Pharmaceuticals, Inc.
Category: prescription | Type: HUMAN PRESCRIPTION DRUG LABEL
Date: 20260120

ACTIVE INGREDIENTS: EMPAGLIFLOZIN 10 mg/1 1; LINAGLIPTIN 5 mg/1 1

HIGHLIGHTS OF PRESCRIBING INFORMATION

These highlights do not include all the information needed to use GLYXAMBI safely and effectively. See full prescribing information for GLYXAMBI.
GLYXAMBI® (empagliflozin and linagliptin tablets), for oral use
Initial U.S. Approval: 2015

RECENT MAJOR CHANGES

Warnings and Precautions (5.4) | 10/2025

1 INDICATIONS AND USAGE

GLYXAMBI is a combination of empagliflozin, a sodium-glucose co-transporter 2 (SGLT2) inhibitor and linagliptin, a dipeptidyl peptidase-4 (DPP-4) inhibitor, indicated as an adjunct to diet and exercise to improve glycemic control in adults with type 2 diabetes mellitus.

Empagliflozin is indicated to reduce the risk of cardiovascular (CV) death in adults with type 2 diabetes mellitus and established CV disease. (1)

Limitations of Use

- Not recommended for use to improve glycemic control in patients with type 1 diabetes mellitus. It may increase the risk of diabetic ketoacidosis in these patients. (1)
- Has not been studied in patients with a history of pancreatitis. (1)
- Not recommended for use to improve glycemic control in adults with type 2 diabetes mellitus with an eGFR less than 30 mL/min/1.73 m^2. (1)

2 DOSAGE AND ADMINISTRATION

- Assess renal function before initiating and as clinically indicated. Assess volume status and correct volume depletion before initiating. (2.1)
- The recommended dosage of GLYXAMBI is 10 mg empagliflozin and 5 mg linagliptin once daily, taken in the morning, with or without food. (2.2)
- Dosage may be increased to 25 mg empagliflozin and 5 mg linagliptin once daily. (2.2)
- Withhold GLYXAMBI for at least 3 days, if possible, prior to surgery or procedures associated with prolonged fasting. (2.4)

3 DOSAGE FORMS AND STRENGTHS

Tablets:

- 10 mg empagliflozin/5 mg linagliptin (3)
- 25 mg empagliflozin/5 mg linagliptin (3)

4 CONTRAINDICATIONS

- Hypersensitivity to empagliflozin, linagliptin, or any of the excipients in GLYXAMBI. (4)

5 WARNINGS AND PRECAUTIONS

- Diabetic Ketoacidosis in Patients with Type 1 Diabetes Mellitus and Other Ketoacidosis: Consider ketone monitoring in patients at risk of ketoacidosis, as indicated. Assess for ketoacidosis regardless of presenting blood glucose levels and discontinue GLYXAMBI if ketoacidosis is suspected. Monitor patients for resolution of ketoacidosis before restarting. (5.1)
- Pancreatitis: There have been reports of acute pancreatitis, including fatal pancreatitis. If pancreatitis is suspected, promptly discontinue GLYXAMBI. (5.2)
- Volume Depletion: Before initiating GLYXAMBI, assess volume status and renal function in patients with impaired renal function, elderly patients, or patients on loop diuretics. Monitor for signs and symptoms during therapy. (5.3)
- Genitourinary Infections, including Urosepsis, Pyelonephritis, Necrotizing Fasciitis of the Perineum (Fournier's Gangrene), and Genital Mycotic Infections: Monitor patients for signs and symptoms of genitourinary infections and treat promptly, if indicated. Immediately evaluate patients presenting with pain or tenderness, erythema, or swelling in the genital or perineal area, along with fever or malaise, for necrotizing fasciitis and if suspected, discontinue GLYXAMBI, and promptly institute appropriate medical and/or surgical intervention. (5.4)
- Hypoglycemia: Consider lowering the dosage of insulin secretagogue or insulin to reduce the risk of hypoglycemia when initiating GLYXAMBI. (5.5)
- Lower Limb Amputation: Monitor patients for infections or ulcers of lower limbs, and institute appropriate treatment. (5.6)
- Hypersensitivity Reactions: Serious hypersensitivity reactions (e.g., anaphylaxis, angioedema, and exfoliative skin conditions) have occurred with empagliflozin and linagliptin. If hypersensitivity reactions occur, discontinue GLYXAMBI, treat promptly, and monitor until signs and symptoms resolve. (5.7)
- Arthralgia: Severe and disabling arthralgia has been reported in patients taking linagliptin. Consider as a possible cause for severe joint pain and discontinue drug if appropriate. (5.8)
- Bullous Pemphigoid: There have been reports of bullous pemphigoid requiring hospitalization. Tell patients to report development of blisters or erosions. If bullous pemphigoid is suspected, discontinue GLYXAMBI. (5.9)
- Heart Failure: Heart failure has been observed with two other members of the DPP-4 inhibitor class. Consider risks and benefits of GLYXAMBI in patients who have known risk factors for heart failure. Monitor for signs and symptoms. (5.10)

6 ADVERSE REACTIONS

Most common adverse reactions (5% or greater incidence) were urinary tract infections, nasopharyngitis, and upper respiratory tract infections (6.1)

To report SUSPECTED ADVERSE REACTIONS, contact Boehringer Ingelheim Pharmaceuticals, Inc. at 1-800-542-6257, or FDA at 1-800-FDA-1088 or www.fda.gov/medwatch.

7 DRUG INTERACTIONS

See full prescribing information for information on drug interactions and interference of GLYXAMBI with laboratory tests. (7)

8 USE IN SPECIFIC POPULATIONS

- Pregnancy: Advise females of the potential risk to a fetus especially during the second and third trimesters. (8.1)
- Lactation: Not recommended when breastfeeding. (8.2)
- Pediatric Patients: Safety and effectiveness of GLYXAMBI in pediatric patients have not been established. (8.4)
- Geriatric Patients: Higher incidence of adverse reactions related to volume depletion and reduced renal function. (8.5)
- Renal Impairment: Higher incidence of adverse reactions related to reduced renal function. (8.6)

FULL PRESCRIBING INFORMATION

1 INDICATIONS AND USAGE

GLYXAMBI is a combination of empagliflozin and linagliptin indicated as an adjunct to diet and exercise to improve glycemic control in adults with type 2 diabetes mellitus.

Empagliflozin is indicated to reduce the risk of cardiovascular (CV) death in adults with type 2 diabetes mellitus and established CV disease [see Clinical Studies (14.2)].

Limitations of Use

GLYXAMBI is not recommended for use to improve glycemic control in patients with type 1 diabetes mellitus. It may increase the risk of diabetic ketoacidosis in these patients [see Warnings and Precautions (5.1)].

GLYXAMBI has not been studied in patients with a history of pancreatitis. It is unknown whether patients with a history of pancreatitis are at an increased risk for the development of pancreatitis while using GLYXAMBI [see Warnings and Precautions (5.2)].

GLYXAMBI is not recommended for use to improve glycemic control in adults with type 2 diabetes mellitus with an eGFR less than 30 mL/min/1.73 m^2. GLYXAMBI is likely to be ineffective in this setting based upon its mechanism of action.

2 DOSAGE AND ADMINISTRATION

2.1 Testing Prior to Initiation of GLYXAMBI

- Assess renal function before initiating GLYXAMBI and as clinically indicated [see Warnings and Precautions (5.3)].
- Assess volume status. In patients with volume depletion, correct this condition before initiating GLYXAMBI [see Warnings and Precautions (5.3) and Use in Specific Populations (8.5, 8.6)].

2.2 Recommended Dosage and Administration

The recommended dosage of GLYXAMBI is 10 mg empagliflozin/5 mg linagliptin once daily in the morning, taken with or without food. GLYXAMBI may be increased to 25 mg empagliflozin/5 mg linagliptin once daily for additional glycemic control.

2.3 Dosage Recommendations in Patients with Renal Impairment

GLYXAMBI is not recommended for use in patients with an eGFR less than 30 mL/min/1.73 m^2 [see Indications and Usage (1), Warnings and Precautions (5.3), and Use in Specific Populations (8.6)].

2.4 Temporary Interruption for Surgery

Withhold GLYXAMBI for at least 3 days, if possible, prior to surgery or procedures associated with prolonged fasting. Resume GLYXAMBI when the patient is clinically stable and has resumed oral intake [see Warnings and Precautions (5.1) and Clinical Pharmacology (12.2)].

2.5 Recommendations Regarding Missed Dose

- If a dose is missed, instruct patients to take the dose as soon as possible.
- Advise patients not to double up the next dose.

3 DOSAGE FORMS AND STRENGTHS

GLYXAMBI tablets available as:

- 10 mg empagliflozin/5 mg linagliptin are pale yellow, arc triangular, flat-faced, bevel-edged, film-coated tablets. One side is debossed with the Boehringer Ingelheim company symbol; the other side is debossed with "10/5".
- 25 mg empagliflozin/5 mg linagliptin are pale pink, arc triangular, flat-faced, bevel-edged, film-coated tablets. One side is debossed with the Boehringer Ingelheim company symbol; the other side is debossed with "25/5".

4 CONTRAINDICATIONS

GLYXAMBI is contraindicated in patients:

- with a hypersensitivity to empagliflozin, linagliptin, or any of the excipients in GLYXAMBI, reactions such as anaphylaxis, angioedema, exfoliative skin conditions, urticaria, or bronchial hyperreactivity have occurred [see Warnings and Precautions (5.7) and Adverse Reactions (6)].

5 WARNINGS AND PRECAUTIONS

5.1 Diabetic Ketoacidosis in Patients with Type 1 Diabetes Mellitus and Other Ketoacidosis

In patients with type 1 diabetes mellitus, empagliflozin, a component of GLYXAMBI, significantly increases the risk of diabetic ketoacidosis, a life-threatening event, beyond the background rate. In placebo-controlled trials of patients with type 1 diabetes mellitus, the risk of ketoacidosis was markedly increased in patients who received sodium glucose co-transporter 2 (SGLT2) inhibitors compared to patients who received placebo and fatal ketoacidosis has occurred with empagliflozin. GLYXAMBI is not indicated for glycemic control in patients with type 1 diabetes mellitus.

Type 2 diabetes mellitus and pancreatic disorders (e.g., history of pancreatitis or pancreatic surgery) are also risk factors for ketoacidosis. There have been postmarketing reports of fatal events of ketoacidosis in patients with type 2 diabetes mellitus using SGLT2 inhibitors, including GLYXAMBI.

Precipitating conditions for diabetic ketoacidosis or other ketoacidosis include under-insulinization due to insulin dose reduction or missed insulin doses, acute febrile illness, reduced caloric intake, ketogenic diet, surgery, volume depletion, and alcohol abuse.

Signs and symptoms are consistent with dehydration and severe metabolic acidosis and include nausea, vomiting, abdominal pain, generalized malaise, and shortness of breath. Blood glucose levels at presentation may be below those typically expected for diabetic ketoacidosis (e.g., less than 250 mg/dL). Ketoacidosis and glucosuria may persist longer than typically expected. Urinary glucose excretion persists for 3 days after discontinuing GLYXAMBI [see Clinical Pharmacology (12.2)]; however, there have been postmarketing reports of ketoacidosis and/or glucosuria lasting greater than 6 days and some up to 2 weeks after discontinuation of SGLT2 inhibitors.

Consider ketone monitoring in patients at risk for ketoacidosis if indicated by the clinical situation. Assess for ketoacidosis regardless of presenting blood glucose levels in patients who present with signs and symptoms consistent with severe metabolic acidosis. If ketoacidosis is suspected, discontinue GLYXAMBI, promptly evaluate, and treat ketoacidosis, if confirmed. Monitor patients for resolution of ketoacidosis before restarting GLYXAMBI.

Withhold GLYXAMBI, if possible, in temporary clinical situations that could predispose patients to ketoacidosis. Resume GLYXAMBI when the patient is clinically stable and has resumed oral intake [see Dosage and Administration (2.4)].

Educate all patients on the signs and symptoms of ketoacidosis and instruct patients to discontinue GLYXAMBI and seek medical attention immediately if signs and symptoms occur.

5.2 Pancreatitis

Acute pancreatitis, including fatal pancreatitis, has been reported in patients treated with linagliptin. In the CARMELINA trial [see Clinical Studies (14.3)], acute pancreatitis was reported in 9 (0.3%) patients treated with linagliptin and in 5 (0.1%) patients treated with placebo. Two patients treated with linagliptin in the CARMELINA trial had acute pancreatitis with a fatal outcome. There have been postmarketing reports of acute pancreatitis, including fatal pancreatitis, in patients treated with linagliptin.

Take careful notice of potential signs and symptoms of pancreatitis. If pancreatitis is suspected, promptly discontinue GLYXAMBI and initiate appropriate management. It is unknown whether patients with a history of pancreatitis are at increased risk for the development of pancreatitis while using GLYXAMBI.

5.3 Volume Depletion

Empagliflozin can cause intravascular volume depletion which may sometimes manifest as symptomatic hypotension or acute transient changes in creatinine [see Adverse Reactions (6.1)]. There have been post-marketing reports of acute kidney injury, some requiring hospitalization and dialysis, in patients with type 2 diabetes mellitus receiving SGLT2 inhibitors, including empagliflozin. Patients with impaired renal function (eGFR less than 60 mL/min/1.73 m^2), elderly patients, or patients on loop diuretics may be at increased risk for volume depletion or hypotension. Before initiating GLYXAMBI in patients with one or more of these characteristics, assess volume status and renal function. In patients with volume depletion, correct this condition before initiating GLYXAMBI. Monitor for signs and symptoms of volume depletion, and renal function after initiating therapy.

5.4 Genitourinary Infections, including Urosepsis, Pyelonephritis, Necrotizing Fasciitis of the Perineum (Fournier's Gangrene), and Genital Mycotic Infections

Empagliflozin increases urinary glucose excretion [see Clinical Pharmacology (12.2)] and increases the risk of genitourinary infections including urinary tract infections and genital mycotic infections in both male and female patients [see Adverse Reactions (6.1)].

Serious genitourinary infections, including urosepsis, pyelonephritis, and necrotizing fasciitis of the perineum (Fournier's gangrene, a rare life-threatening infection requiring urgent surgical intervention), have occurred in patients with or without diabetes mellitus receiving SGLT2 inhibitors, including empagliflozin [see Adverse Reactions (6.2)]. Cases have required hospitalization. In patients with Fournier's gangrene, serious outcomes have included multiple surgeries and death. GLYXAMBI is only indicated for use in patients with type 2 diabetes mellitus.

Patients with a history of chronic or recurrent genitourinary infections are more likely to develop genitourinary infections when using GLYXAMBI. Monitor patients for signs and symptoms of genitourinary infections and treat promptly, if indicated.

Immediately evaluate patients presenting with pain or tenderness, erythema, or swelling in the genital or perineal area, along with fever or malaise, for necrotizing fasciitis. If suspected, discontinue GLYXAMBI and promptly institute appropriate medical and/or surgical intervention.

5.5 Hypoglycemia with Concomitant Use with Insulin and Insulin Secretagogues

Insulin and insulin secretagogues are known to cause hypoglycemia. The risk of hypoglycemia is increased when GLYXAMBI is used in combination with an insulin secretagogue (e.g., sulfonylurea) or insulin. Therefore, a lower dosage of the insulin secretagogue or insulin may be required to reduce the risk of hypoglycemia when used in combination with GLYXAMBI.

5.6 Lower Limb Amputation

In some clinical studies with SGLT2 inhibitors an imbalance in the incidence of lower limb amputation has been observed. Across four empagliflozin outcome trials, lower limb amputation event rates were 4.3 and 5.0 events per 1,000 patient-years in the placebo group and the empagliflozin 10 mg or 25 mg dose group, respectively, with a HR of 1.05 (95 % CI) (0.81, 1.36).

In a long-term cardio-renal outcome trial, in patients with chronic kidney disease, the occurrence of lower limb amputations was reported with event rates of 2.9, and 4.3 events per 1,000 patient-years in the placebo, and empagliflozin 10 mg treatment arms, respectively. Amputation of the toe and mid-foot were most frequent (21 out of 28 empagliflozin 10 mg treated patients with lower limb amputations), and some involving above and below the knee. Some patients had multiple amputations. GLYXAMBI is not indicated for the treatment of chronic kidney disease.

Peripheral artery disease, and diabetic foot infection (including osteomyelitis), were the most common precipitating medical events leading to the need for an amputation. The risk of amputation was highest in patients with a baseline history of diabetic foot, peripheral artery disease (including previous amputation) or diabetes.

Counsel patients about the importance of routine preventative foot care. Monitor patients receiving GLYXAMBI for signs and symptoms of diabetic foot infection (including osteomyelitis), new pain or tenderness, sores or ulcers involving the lower limbs, and institute appropriate treatment.

5.7 Hypersensitivity Reactions

There have been postmarketing reports of serious hypersensitivity reactions in patients treated with linagliptin. These reactions include anaphylaxis, angioedema, and exfoliative skin conditions. Onset of these reactions occurred predominantly within the first 3 months after initiation of treatment with linagliptin, with some reports occurring after the first dose.

Angioedema has also been reported with other dipeptidyl peptidase-4 (DPP-4) inhibitors. Use caution in a patient with a history of angioedema to another DPP-4 inhibitor because it is unknown whether such patients will be predisposed to angioedema with GLYXAMBI.

There have been postmarketing reports of serious hypersensitivity reactions, (e.g., angioedema) in patients treated with empagliflozin.

If a hypersensitivity reaction occurs, discontinue GLYXAMBI, treat promptly per standard of care, and monitor until signs and symptoms resolve. GLYXAMBI is contraindicated in patients with hypersensitivity to linagliptin, empagliflozin or any of the excipients in GLYXAMBI [see Contraindications (4)].

5.8 Severe and Disabling Arthralgia

There have been postmarketing reports of severe and disabling arthralgia in patients taking linagliptin. The time to onset of symptoms following initiation of drug therapy varied from one day to years. Patients experienced relief of symptoms upon discontinuation of the medication. A subset of patients experienced a recurrence of symptoms when restarting the same drug or a different DPP-4 inhibitor. Consider DPP-4 inhibitors as a possible cause for severe joint pain and discontinue drug if appropriate.

5.9 Bullous Pemphigoid

Bullous pemphigoid was reported in 7 (0.2%) patients treated with linagliptin compared to none in patients treated with placebo in the CARMELINA trial [see Clinical Studies (14.3)], and 3 of these patients were hospitalized due to bullous pemphigoid. Postmarketing cases of bullous pemphigoid requiring hospitalization have been reported with DPP-4 inhibitor use. In reported cases, patients typically recovered with topical or systemic immunosuppressive treatment and discontinuation of the DPP-4 inhibitor. Tell patients to report development of blisters or erosions while receiving GLYXAMBI. If bullous pemphigoid is suspected, GLYXAMBI should be discontinued and referral to a dermatologist should be considered for diagnosis and appropriate treatment.

5.10 Heart Failure

An association between DPP-4 inhibitor treatment and heart failure has been observed in cardiovascular outcomes trials for two other members of the DPP-4 inhibitor class. These trials evaluated patients with type 2 diabetes mellitus and atherosclerotic cardiovascular disease.

Consider the risks and benefits of GLYXAMBI prior to initiating treatment in patients at risk for heart failure, such as those with a prior history of heart failure and a history of renal impairment, and observe these patients for signs and symptoms of heart failure during therapy. Advise patients of the characteristic symptoms of heart failure and to immediately report such symptoms. If heart failure develops, evaluate and manage according to current standards of care and consider discontinuation of GLYXAMBI.

6 ADVERSE REACTIONS

The following important adverse reactions are described below and elsewhere in the labeling:

- Diabetic Ketoacidosis in Patients with Type 1 Diabetes Mellitus and Other Ketoacidosis [see Warnings and Precautions (5.1)]
- Pancreatitis [see Warnings and Precautions (5.2)]
- Volume Depletion [see Warnings and Precautions (5.3)]
- Genitourinary Infections, including Urosepsis, Pyelonephritis, Necrotizing Fasciitis of the Perineum (Fournier's Gangrene), and Genital Mycotic Infections [see Warnings and Precautions (5.4)]
- Hypoglycemia with Concomitant Use with Insulin and Insulin Secretagogues [see Warnings and Precautions (5.5)]
- Lower Limb Amputation [see Warnings and Precautions (5.6)]
- Hypersensitivity Reactions [see Warnings and Precautions (5.7)]
- Severe and Disabling Arthralgia [see Warnings and Precautions (5.8)]
- Bullous Pemphigoid [see Warnings and Precautions (5.9)]
- Heart Failure [see Warnings and Precautions (5.10)]

6.1 Clinical Trials Experience

Because clinical trials are conducted under widely varying conditions, adverse reaction rates observed in the clinical trials of a drug cannot be directly compared to rates in the clinical trials of another drug and may not reflect the rates observed in practice.

Empagliflozin and Linagliptin

The safety of concomitantly administered empagliflozin (daily dosage 10 mg or 25 mg) and linagliptin (daily dosage 5 mg) has been evaluated in a total of 1,363 patients with type 2 diabetes mellitus treated for up to 52 weeks in active-controlled clinical trials. The most common adverse reactions with concomitant administration of empagliflozin and linagliptin based on a pooled analyses of these trials are shown in Table 1.

Table 1 Adverse Reactions Reported in ≥5% of Patients Treated with Empagliflozin and Linagliptin
Adverse Reactions | GLYXAMBI (%) 10 mg/5 mg n=272 | GLYXAMBI (%) 25 mg/5 mg n=273
Urinary tract infectiona | 12.5 | 11.4
Nasopharyngitis | 5.9 | 6.6
Upper respiratory tract infection | 7.0 | 7.0
aPredefined adverse event grouping, including, but not limited to, urinary tract infection, asymptomatic bacteriuria, cystitis

Empagliflozin

Adverse reactions that occurred in ≥2% of patients receiving empagliflozin and more commonly than in patients given placebo included (10 mg, 25 mg, and placebo): urinary tract infection (9.3%, 7.6%, and 7.6%), female genital mycotic infections (5.4%, 6.4%, and 1.5%), upper respiratory tract infection (3.1%, 4.0%, and 3.8%), increased urination (3.4%, 3.2%, and 1.0%), dyslipidemia (3.9%, 2.9%, and 3.4%), arthralgia (2.4%, 2.3%, and 2.2%), male genital mycotic infections (3.1%, 1.6%, and 0.4%), and nausea (2.3%, 1.1%, and 1.4%).

Thirst (including polydipsia) was reported in 0%, 1.7%, and 1.5% for placebo, empagliflozin 10 mg, and empagliflozin 25 mg, respectively.

Empagliflozin causes an osmotic diuresis, which may lead to intravascular volume contraction and adverse reactions related to volume depletion. Events related to volume depletion (hypotension and syncope) were reported in 3 patients (1.1%) treated with GLYXAMBI plus metformin.

Linagliptin

Adverse reactions reported in ≥2% of patients treated with linagliptin 5 mg and more commonly than in patients treated with placebo included: nasopharyngitis (7.0% and 6.1%), diarrhea (3.3% and 3.0%), and cough (2.1% and 1.4%).

Other adverse reactions reported in clinical trials with treatment of linagliptin monotherapy were hypersensitivity (e.g., urticaria, angioedema, localized skin exfoliation, or bronchial hyperreactivity) and myalgia.

In the clinical trial program, pancreatitis was reported in 15.2 cases per 10,000 patient year exposure while being treated with linagliptin compared with 3.7 cases per 10,000 patient year exposure while being treated with comparator (placebo and active comparator, sulfonylurea). Three additional cases of pancreatitis were reported following the last administered dose of linagliptin.

Other Adverse Reactions

Hypoglycemia

Empagliflozin and Linagliptin

Table 2 summarizes the reports of hypoglycemia with empagliflozin and linagliptin over a treatment period of 52 weeks.

Table 2 Incidence of Overalla and Severeb Hypoglycemic Adverse Reactions
Add-on to Metformin (52 weeks) | GLYXAMBI (%) 10 mg/5 mg (n=136) | GLYXAMBI (%) 25 mg/5 mg (n=137)
Overall | 2.2 | 3.6
Severe | 0 | 0
aOverall hypoglycemic events: plasma or capillary glucose of less than or equal to 70 mg/dL or requiring assistance
bSevere hypoglycemic events: requiring assistance regardless of blood glucose

Empagliflozin

- Genital Mycotic Infections: In the pool of five placebo-controlled clinical trials, the incidence of genital mycotic infections (e.g., vaginal mycotic infection, vaginal infection, genital infection fungal, vulvovaginal candidiasis, and vulvitis) was increased in patients treated with empagliflozin compared to placebo, occurring in 0.9%, 4.1%, and 3.7% of patients randomized to placebo, empagliflozin 10 mg, and empagliflozin 25 mg, respectively. Discontinuation from trial due to genital infection occurred in 0% of placebo-treated patients and 0.2% of patients treated with either empagliflozin 10 mg or 25 mg.
  Genital mycotic infections occurred more frequently in female than male patients.
  Phimosis occurred more frequently in male patients treated with empagliflozin 10 mg (less than 0.1%) and empagliflozin 25 mg (0.1%) than placebo (0%).
- Urinary Tract Infections: In the pool of five placebo-controlled clinical trials, the incidence of urinary tract infections (e.g., urinary tract infection, asymptomatic bacteriuria, and cystitis) was increased in patients treated with empagliflozin compared to placebo. Patients with a history of chronic or recurrent urinary tract infections were more likely to experience a urinary tract infection. The rate of treatment discontinuation due to urinary tract infections was 0.1%, 0.2%, and 0.1% for placebo, empagliflozin 10 mg, and empagliflozin 25 mg, respectively.
  Urinary tract infections occurred more frequently in female patients. The incidence of urinary tract infections in female patients randomized to placebo, empagliflozin 10 mg, and empagliflozin 25 mg was 16.6%, 18.4%, and 17.0%, respectively. The incidence of urinary tract infections in male patients randomized to placebo, empagliflozin 10 mg, and empagliflozin 25 mg was 3.2%, 3.6%, and 4.1%, respectively [see Use in Specific Populations (8.5)].
- Lower Limb Amputations: Across four empagliflozin outcome trials, lower limb amputation event rates were 4.3 and 5.0 events per 1,000 patient-years in the placebo group and the empagliflozin 10 mg or 25 mg dose group, respectively, with a HR of 1.05 (95% CI) (0.81, 1.36). In a long-term cardio-renal outcome trial, in patients with chronic kidney disease, the occurrence of lower limb amputations was reported with event rates of 2.9, and 4.3 events per 1,000 patient-years in the placebo, and empagliflozin 10 mg treatment arms, respectively. GLYXAMBI is not indicated for the treatment of chronic kidney disease.

Laboratory Test Abnormalities in Clinical Trials of Empagliflozin or Linagliptin

Empagliflozin and Linagliptin

Changes in laboratory findings in patients treated with the combination of empagliflozin and linagliptin included increases in cholesterol and hematocrit compared to baseline.

Empagliflozin

Increases in Serum Creatinine and Decreases in eGFR: Initiation of empagliflozin causes an increase in serum creatinine and decrease in eGFR within weeks of starting therapy and then these changes stabilize. In a trial of patients with moderate renal impairment, larger mean changes were observed. In a long-term CV outcomes trial, the increase in serum creatinine and decrease in eGFR generally did not exceed 0.1 mg/dL and -9.0 mL/min/1.73 m^2, respectively, at Week 4, and reversed after treatment discontinuation, suggesting acute hemodynamic changes may play a role in the renal function changes observed with empagliflozin.

Increase in Low-Density Lipoprotein Cholesterol (LDL-C): Dose-related increases in low-density lipoprotein cholesterol (LDL-C) were observed in patients treated with empagliflozin. LDL-C increased by 2.3%, 4.6%, and 6.5% in patients treated with placebo, empagliflozin 10 mg, and empagliflozin 25 mg, respectively. The range of mean baseline LDL-C levels was 90.3 to 90.6 mg/dL across treatment groups.

Increase in Hematocrit: Median hematocrit decreased by 1.3% in placebo and increased by 2.8% in empagliflozin 10 mg and 2.8% in empagliflozin 25 mg treated patients. At the end of treatment, 0.6%, 2.7%, and 3.5% of patients with hematocrits initially within the reference range had values above the upper limit of the reference range with placebo, empagliflozin 10 mg, and empagliflozin 25 mg, respectively.

Linagliptin

Increase in Uric Acid: Changes in laboratory values that occurred more frequently in the linagliptin group and ≥1% more than in the placebo group were increases in uric acid (1.3% in the placebo group, 2.7% in the linagliptin group).

Increase in Lipase: In a placebo-controlled clinical trial with linagliptin in type 2 diabetes mellitus patients with micro- or macroalbuminuria, a mean increase of 30% in lipase concentrations from baseline to 24 weeks was observed in the linagliptin arm compared to a mean decrease of 2% in the placebo arm. Lipase levels above 3 times upper limit of normal were seen in 8.2% compared to 1.7% patients in the linagliptin and placebo arms, respectively.

Increase in Amylase: In a CV safety trial comparing linagliptin versus glimepiride in patients with type 2 diabetes mellitus, amylase levels above 3 times upper limit of normal were seen in 1.0% compared to 0.5% of patients in the linagliptin and glimepiride arms, respectively.

The clinical significance of elevations in lipase and amylase with linagliptin is unknown in the absence of other signs and symptoms of pancreatitis [see Warnings and Precautions (5.2)].

6.2 Postmarketing Experience

Additional adverse reactions have been identified during postapproval use of linagliptin and empagliflozin. Because these reactions are reported voluntarily from a population of uncertain size, it is generally not possible to reliably estimate their frequency or establish a causal relationship to drug exposure.

Gastrointestinal Disorders: Acute pancreatitis, including fatal pancreatitis [see Indications and Usage (1)], constipation, mouth ulceration, stomatitis

Immune System Disorders: Hypersensitivity reactions including anaphylaxis, angioedema, and exfoliative skin conditions

Infections: Necrotizing fasciitis of the perineum (Fournier's gangrene), urosepsis and pyelonephritis

Metabolism and Nutrition Disorders: Ketoacidosis

Musculoskeletal and Connective Tissue Disorders: Rhabdomyolysis, severe and disabling arthralgia

Renal and Urinary Disorders: Acute kidney injury

Skin and Subcutaneous Tissue Disorders: Bullous pemphigoid, skin reactions (e.g., rash, urticaria)

7 DRUG INTERACTIONS

Table 3 describes clinically relevant interactions with GLYXAMBI.

Table 3 Clinically Relevant Interactions with GLYXAMBI
Diuretics
Clinical Impact | Coadministration of empagliflozin with diuretics resulted in increased urine volume and frequency of voids, which might enhance the potential for volume depletion.
Intervention | Before initiating GLYXAMBI, assess volume status and renal function. In patients with volume depletion, correct this condition before initiating GLYXAMBI. Monitor for signs and symptoms of volume depletion, and renal function after initiating therapy.
Insulin or Insulin Secretagogues
Clinical Impact | The risk of hypoglycemia is increased when GLYXAMBI is used in combination with an insulin secretagogue (e.g., sulfonylurea) or insulin.
Intervention | Coadministration of GLYXAMBI with an insulin secretagogue (e.g., sulfonylurea) or insulin may require lower dosages of the insulin secretagogue or insulin to reduce the risk of hypoglycemia.
Lithium
Clinical Impact | Concomitant use of an SGLT2 inhibitor with lithium may decrease serum lithium concentrations.
Intervention | Monitor serum lithium concentration more frequently during GLYXAMBI initiation and dosage changes.
Inducers of P-glycoprotein or CYP3A4 Enzymes
Clinical Impact | Rifampin decreased linagliptin exposure, suggesting that the efficacy of linagliptin may be reduced when administered in combination with a strong P-gp or CYP3A4 inducer.
Intervention | Use of alternative treatments is strongly recommended when linagliptin is to be administered with a strong P-gp or CYP3A4 inducer.
Positive Urine Glucose Test
Clinical Impact | SGLT2 inhibitors increase urinary glucose excretion and will lead to positive urine glucose tests.
Intervention | Monitoring glycemic control with urine glucose tests is not recommended in patients taking SGLT2 inhibitors. Use alternative methods to monitor glycemic control.
Interference with 1,5-anhydroglucitol (1,5-AG) Assay
Clinical Impact | Measurements of 1,5-AG are unreliable in assessing glycemic control in patients taking SGLT2 inhibitors.
Intervention | Monitoring glycemic control with 1,5-AG assay is not recommended. Use alternative methods to monitor glycemic control.

8 USE IN SPECIFIC POPULATIONS

8.1 Pregnancy

Risk Summary

Based on animal data showing adverse renal effects from empagliflozin, GLYXAMBI is not recommended during the second and third trimesters of pregnancy.

The limited available data with GLYXAMBI, linagliptin, or empagliflozin in pregnant women are not sufficient to determine a drug-associated risk for major birth defects and miscarriage. There are risks to the mother and fetus associated with poorly controlled diabetes in pregnancy (see Clinical Considerations).

In animal studies, empagliflozin, a component of GLYXAMBI, resulted in adverse renal changes in rats when administered during a period of renal development corresponding to the late second and third trimesters of human pregnancy. Doses approximately 13-times the maximum clinical dose caused renal pelvic and tubule dilatations that were reversible. No adverse developmental effects were observed when the combination of linagliptin and empagliflozin was administered to pregnant rats (see Data).

The estimated background risk of major birth defects is 6% to 10% in women with pre-gestational diabetes with a HbA1c >7 and has been reported to be as high as 20% to 25% in women with HbA1c >10. The estimated background risk of miscarriage for the indicated population is unknown. In the U.S. general population, the estimated background risk of major birth defects and miscarriage in clinically recognized pregnancies is 2% to 4% and 15% to 20%, respectively.

Clinical Considerations

Disease-associated maternal and/or embryo/fetal risk

Poorly controlled diabetes in pregnancy increases the maternal risk for diabetic ketoacidosis, pre-eclampsia, spontaneous abortions, preterm delivery, and delivery complications. Poorly controlled diabetes increases the fetal risk for major birth defects, stillbirth, and macrosomia related morbidity.

Data

Animal Data

The combined components administered during the period of organogenesis were not teratogenic in rats up to and including a combined dose of 700 mg/kg/day empagliflozin and 140 mg/kg/day linagliptin, which is 253- and 353-times the clinical exposure. A pre- and postnatal development study was not conducted with the combined components of GLYXAMBI.

Empagliflozin: Empagliflozin dosed directly to juvenile rats from postnatal day (PND) 21 until PND 90 at doses of 1, 10, 30, and 100 mg/kg/day caused increased kidney weights and renal tubular and pelvic dilatation at 100 mg/kg/day, which approximates 13-times the maximum clinical dose of 25 mg, based on AUC. These findings were not observed after a 13-week, drug-free recovery period. These outcomes occurred with drug exposure during periods of renal development in rats that correspond to the late second and third trimester of human renal development.

In embryo-fetal development studies in rats and rabbits, empagliflozin was administered for intervals coinciding with the first trimester period of organogenesis in humans. Doses up to 300 mg/kg/day, which approximates 48-times (rats) and 128-times (rabbits) the maximum clinical dose of 25 mg (based on AUC), did not result in adverse developmental effects. In rats, at higher doses of empagliflozin causing maternal toxicity, malformations of limb bones increased in fetuses at 700 mg/kg/day or 154-times the 25 mg maximum clinical dose. Empagliflozin crosses the placenta and reaches fetal tissues in rats. In the rabbit, higher doses of empagliflozin resulted in maternal and fetal toxicity at 700 mg/kg/day, or 139-times the 25 mg maximum clinical dose.

In pre- and postnatal development studies in pregnant rats, empagliflozin was administered from gestation day 6 through to lactation day 20 (weaning) at up to 100 mg/kg/day (approximately 16-times the 25 mg maximum clinical dose) without maternal toxicity. Reduced body weight was observed in the offspring at greater than or equal to 30 mg/kg/day (approximately 4-times the 25 mg maximum clinical dose).

Linagliptin: No adverse developmental outcome was observed when linagliptin was administered to pregnant Wistar Han rats and Himalayan rabbits during the period of organogenesis at doses up to 240 mg/kg/day and 150 mg/kg/day, respectively. These doses represent approximately 943-times (rats) and 1,943-times (rabbits) the 5 mg maximum clinical dose, based on exposure. No adverse functional, behavioral, or reproductive outcome was observed in offspring following administration of linagliptin to Wistar Han rats from gestation day 6 to lactation day 21 at a dose 49-times the maximum recommended human dose, based on exposure.

Linagliptin crosses the placenta into the fetus following oral dosing in pregnant rats and rabbits.

8.2 Lactation

Risk Summary

There is limited information regarding the presence of GLYXAMBI, or its individual components in human milk, the effects on the breastfed infant, or the effects on milk production. Empagliflozin and linagliptin are present in rat milk (see Data). Since human kidney maturation occurs in utero and during the first 2 years of life when lactational exposure may occur, there may be risk to the developing human kidney.

Because of the potential for serious adverse reactions in a breastfed infant, including the potential for empagliflozin to affect postnatal renal development, advise patients that use of GLYXAMBI is not recommended while breastfeeding.

Data

Empagliflozin was present at a low level in rat fetal tissues after a single oral dose to the dams at gestation day 18. In rat milk, the mean milk to plasma ratio ranged from 0.634 to 5, and was greater than one from 2 to 24 hours post-dose. The mean maximal milk to plasma ratio of 5 occurred at 8 hours post-dose, suggesting accumulation of empagliflozin in the milk. Juvenile rats directly exposed to empagliflozin showed a risk to the developing kidney (renal pelvic and tubular dilatations) during maturation.

8.4 Pediatric Use

Safety and effectiveness of GLYXAMBI have not been established in pediatric patients.

8.5 Geriatric Use

GLYXAMBI

Empagliflozin is associated with osmotic diuresis, which could affect hydration status of patients age 75 years and older [see Warnings and Precautions (5.3)].

Empagliflozin

In empagliflozin type 2 diabetes mellitus trials, 2,721 empagliflozin-treated patients were 65 years of age and older and 491 patients were 75 years of age and older. In these trials, volume depletion-related adverse reactions occurred in 2.1%, 2.3%, and 4.4% of patients 75 years of age and older in the placebo, empagliflozin 10 mg, and empagliflozin 25 mg once daily groups, respectively; and urinary tract infections occurred in 10.5%, 15.7%, and 15.1% of patients 75 years of age and older in the placebo, empagliflozin 10 mg, and empagliflozin 25 mg once daily groups, respectively.

Linagliptin

In linagliptin trials, 1,085 linagliptin-treated patients were 65 years of age and older and 131 patients were 75 years of age and older. In these linagliptin trials, no overall differences in safety or effectiveness of linagliptin were observed between geriatric patients and younger adult patients.

8.6 Renal Impairment

Empagliflozin

The glucose lowering benefit of empagliflozin 25 mg decreased in patients with worsening renal function. The risks of renal impairment [see Warnings and Precautions (5.3)], volume depletion adverse reactions and urinary tract infection-related adverse reactions increased with worsening renal function.

Efficacy and safety trials with empagliflozin for glycemic control and the EMPA-REG OUTCOME trial did not enroll patients with ESRD on dialysis or patients with an eGFR less than 30 mL/min/1.73 m^2. [see Indications and Usage (1)].

8.7 Hepatic Impairment

GLYXAMBI may be used in patients with hepatic impairment [see Clinical Pharmacology (12.3)].

10 OVERDOSAGE

In the event of an overdose with GLYXAMBI, consider contacting the Poison Help line (1-800-222-1222) or a medical toxicologist for additional overdosage management recommendations. Removal of empagliflozin by hemodialysis has not been studied, and removal of linagliptin by hemodialysis or peritoneal dialysis is unlikely.

11 DESCRIPTION

GLYXAMBI tablets for oral use contain: empagliflozin and linagliptin.

Empagliflozin

Empagliflozin is an inhibitor of the SGLT2.

The chemical name of empagliflozin is D-Glucitol,1,5-anhydro-1-C-[4-chloro-3-[[4-[[(3S)-tetrahydro-3-furanyl]oxy]phenyl]methyl]phenyl]-, (1S).

The molecular formula is C23H27ClO7 and the molecular weight is 450.91. The structural formula is:

Empagliflozin is a white to yellowish, non-hygroscopic powder. It is very slightly soluble in water, sparingly soluble in methanol, slightly soluble in ethanol and acetonitrile, soluble in 50% acetonitrile/water, and practically insoluble in toluene.

Linagliptin

Linagliptin is an inhibitor of the DPP-4 enzyme.

The chemical name of linagliptin is 1H-Purine-2,6-dione, 8-[(3R)-3-amino-1-piperidinyl]-7-(2-butyn-1-yl)-3,7-dihydro-3-methyl-1-[(4-methyl-2-quinazolinyl)methyl]-

The molecular formula is C25H28N8O2 and the molecular weight is 472.54. The structural formula is:

Linagliptin is a white to yellowish, not or only slightly hygroscopic solid substance. It is very slightly soluble in water. Linagliptin is soluble in methanol, sparingly soluble in ethanol, very slightly soluble in isopropanol, and very slightly soluble in acetone.

GLYXAMBI

GLYXAMBI tablets are available in two dosage strengths containing 10 mg or 25 mg empagliflozin in combination with 5 mg linagliptin. The inactive ingredients of GLYXAMBI are the following: Tablet Core: copovidone, corn starch, crospovidone, magnesium stearate, mannitol, pregelatinized starch, and talc. Coating: ferric oxide yellow (10 mg/5 mg) or ferric oxide red (25 mg/5 mg), hypromellose, mannitol, polyethylene glycol, talc, and titanium dioxide.

12 CLINICAL PHARMACOLOGY

12.1 Mechanism of Action

GLYXAMBI

GLYXAMBI contains: empagliflozin, a SGLT2 inhibitor, and linagliptin, a DPP-4 inhibitor.

Empagliflozin

Empagliflozin is an inhibitor of SGLT2, the predominant transporter responsible for reabsorption of glucose from the glomerular filtrate back into the circulation. By inhibiting SGLT2, empagliflozin reduces renal reabsorption of filtered glucose and lowers the renal threshold for glucose, and thereby increases urinary glucose excretion.

Linagliptin

Linagliptin is an inhibitor of DPP-4, an enzyme that degrades the incretin hormones glucagon-like peptide-1 (GLP-1) and glucose-dependent insulinotropic polypeptide (GIP). Thus, linagliptin increases the concentrations of active incretin hormones, stimulating the release of insulin in a glucose-dependent manner and decreasing the levels of glucagon in the circulation. Both incretin hormones are involved in the physiological regulation of glucose homeostasis. Incretin hormones are secreted at a low basal level throughout the day and levels rise immediately after meal intake. GLP-1 and GIP increase insulin biosynthesis and secretion from pancreatic beta cells in the presence of normal and elevated blood glucose levels. Furthermore, GLP-1 also reduces glucagon secretion from pancreatic alpha cells, resulting in a reduction in hepatic glucose output.

12.2 Pharmacodynamics

Empagliflozin

Urinary Glucose Excretion

In patients with type 2 diabetes mellitus, urinary glucose excretion increased immediately following a dose of empagliflozin and was maintained at the end of a 4-week treatment period averaging at approximately 64 grams per day with 10 mg empagliflozin and 78 grams per day with 25 mg empagliflozin once daily. Data from single oral doses of empagliflozin in healthy subjects indicate that, on average, the elevation in urinary glucose excretion approaches baseline by about 3 days for the 10 mg and 25 mg doses.

Urinary Volume

In a 5-day study, mean 24-hour urine volume increase from baseline was 341 mL on Day 1 and 135 mL on Day 5 of empagliflozin 25 mg once daily treatment.

Cardiac Electrophysiology

In a randomized, placebo-controlled, active-comparator, crossover study, 30 healthy subjects were administered a single oral dose of empagliflozin 25 mg, empagliflozin 200 mg (8 times the maximum recommended dose), moxifloxacin, and placebo. No increase in QTc was observed with either 25 mg or 200 mg empagliflozin.

Linagliptin

Linagliptin binds to DPP-4 in a reversible manner and increases the concentrations of incretin hormones. Linagliptin glucose-dependently increases insulin secretion and lowers glucagon secretion, thus resulting in a better regulation of the glucose homeostasis. Linagliptin binds selectively to DPP-4 and selectively inhibits DPP-4, but not DPP-8 or DPP-9 activity in vitro at concentrations approximating therapeutic exposures.

Cardiac Electrophysiology

In a randomized, placebo-controlled, active-comparator, 4-way crossover study, 36 healthy subjects were administered a single oral dose of linagliptin 5 mg, linagliptin 100 mg (20 times the recommended dose), moxifloxacin, and placebo. No increase in QTc was observed with either the recommended dose of 5 mg or the 100 mg dose. At the 100 mg dose, peak linagliptin plasma concentrations were approximately 38-fold higher than the peak concentrations following a 5-mg dose.

12.3 Pharmacokinetics

GLYXAMBI

Administration of the fixed-dose combination with food resulted in no change in overall exposure of empagliflozin or linagliptin; however, the peak exposure was decreased 39% and 32% for empagliflozin and linagliptin, respectively. These changes are not likely to be clinically significant.

Empagliflozin

The pharmacokinetics of empagliflozin has been characterized in healthy volunteers and patients with type 2 diabetes mellitus and no clinically relevant differences were noted between the two populations. The steady-state mean plasma AUC and Cmax were 1,870 nmol∙h/L and 259 nmol/L, respectively, with 10 mg empagliflozin once daily treatment, and 4,740 nmol∙h/L and 687 nmol/L, respectively, with 25 mg empagliflozin once daily treatment. Systemic exposure of empagliflozin increased in a dose-proportional manner in the therapeutic dose range. Empagliflozin does not appear to have time-dependent pharmacokinetic characteristics. Following once-daily dosing, up to 22% accumulation, with respect to plasma AUC, was observed at steady-state.

Absorption

After oral administration, peak plasma concentrations of empagliflozin were reached at 1.5 hours post-dose. Administration of 25 mg empagliflozin after intake of a high-fat and high-calorie meal resulted in slightly lower exposure; AUC decreased by approximately 16% and Cmax decreased by approximately 37%, compared to fasted condition. The observed effect of food on empagliflozin pharmacokinetics was not considered clinically relevant and empagliflozin may be administered with or without food.

Distribution

The apparent steady-state volume of distribution was estimated to be 73.8 L based on a population pharmacokinetic analysis. Following administration of an oral [^14C]-empagliflozin solution to healthy subjects, the red blood cell partitioning was approximately 36.8% and plasma protein binding was 86.2%.

Elimination

The apparent terminal elimination half-life of empagliflozin was estimated to be 12.4 h and apparent oral clearance was 10.6 L/h based on the population pharmacokinetic analysis.

Metabolism

No major metabolites of empagliflozin were detected in human plasma and the most abundant metabolites were three glucuronide conjugates (2-O-, 3-O-, and 6-O-glucuronide). Systemic exposure of each metabolite was less than 10% of total drug-related material. In vitro studies suggested that the primary route of metabolism of empagliflozin in humans is glucuronidation by the uridine 5'-diphospho-glucuronosyltransferases UGT2B7, UGT1A3, UGT1A8, and UGT1A9.

Excretion

Following administration of an oral [^14C]-empagliflozin solution to healthy subjects, approximately 95.6% of the drug-related radioactivity was eliminated in feces (41.2%) or urine (54.4%). The majority of drug-related radioactivity recovered in feces was unchanged parent drug and approximately half of drug-related radioactivity excreted in urine was unchanged parent drug.

Linagliptin

Absorption

The absolute bioavailability of linagliptin is approximately 30%. A high-fat meal reduced Cmax by 15% and increased AUC by 4%; this effect is not clinically relevant. Linagliptin may be administered with or without food.

Distribution

The mean apparent volume of distribution at steady-state following a single intravenous dose of linagliptin 5 mg to healthy subjects is approximately 1,110 L, indicating that linagliptin extensively distributes to the tissues. Plasma protein binding of linagliptin is concentration-dependent, decreasing from about 99% at 1 nmol/L to 75% to 89% at ≥30 nmol/L, reflecting saturation of binding to DPP-4 with increasing concentration of linagliptin. At high concentrations, where DPP-4 is fully saturated, 70% to 80% of linagliptin remains bound to plasma proteins and 20% to 30% is unbound in plasma. Plasma binding is not altered in patients with renal or hepatic impairment.

Elimination

Linagliptin has a terminal half-life of about 200 hours at steady-state, though the accumulation half-life is about 11 hours. Renal clearance at steady-state was approximately 70 mL/min.

Metabolism

Following oral administration, the majority (about 90%) of linagliptin is excreted unchanged, indicating that metabolism represents a minor elimination pathway. A small fraction of absorbed linagliptin is metabolized to a pharmacologically inactive metabolite, which shows a steady-state exposure of 13.3% relative to linagliptin.

Excretion

Following administration of an oral [^14C]-linagliptin dose to healthy subjects, approximately 85% of the administered radioactivity was eliminated via the enterohepatic system (80%) or urine (5%) within 4 days of dosing.

Specific Populations

Effects of Age, Body Mass Index, Gender, and Race

Empagliflozin: Age, body mass index (BMI), gender and race (Asians versus primarily Whites) do not have a clinically meaningful effect on pharmacokinetics of empagliflozin.

Linagliptin: Based on the population PK analysis, age, body mass index (BMI), gender and race do not have a clinically meaningful effect on pharmacokinetics of linagliptin [see Use in Specific Populations (8.5)].

Patients with Renal Impairment

GLYXAMBI: Studies characterizing the pharmacokinetics of empagliflozin and linagliptin after administration of GLYXAMBI in renally impaired patients have not been performed.

Empagliflozin: In patients with mild (eGFR: 60 to less than 90 mL/min/1.73 m^2), moderate (eGFR: 30 to less than 60 mL/min/1.73 m^2), and severe (eGFR: less than 30 mL/min/1.73 m^2) renal impairment and patients on dialysis due to kidney failure, AUC of empagliflozin increased by approximately 18%, 20%, 66%, and 48%, respectively, compared to subjects with normal renal function. Peak plasma levels of empagliflozin were similar in patients with moderate renal impairment and patients on dialysis due to kidney failure compared to subjects with normal renal function. Peak plasma levels of empagliflozin were roughly 20% higher in patients with mild and severe renal impairment as compared to subjects with normal renal function. Population pharmacokinetic analysis showed that the apparent oral clearance of empagliflozin decreased, with a decrease in eGFR leading to an increase in drug exposure. However, the fraction of empagliflozin that was excreted unchanged in urine, and urinary glucose excretion, declined with decrease in eGFR.

Linagliptin: An open-label pharmacokinetic study evaluated the pharmacokinetics of linagliptin 5 mg in male and female patients with varying degrees of chronic renal impairment. The study included 6 healthy subjects with normal renal function (creatinine clearance [CrCl] ≥80 mL/min), 6 patients with mild renal impairment (CrCl 50 to <80 mL/min), 6 patients with moderate renal impairment (CrCl 30 to <50 mL/min), 10 patients with type 2 diabetes mellitus and severe renal impairment (CrCl <30 mL/min), and 11 patients with type 2 diabetes mellitus and normal renal function. Creatinine clearance was measured by 24-hour urinary creatinine clearance measurements or estimated from serum creatinine based on the Cockcroft-Gault formula.

Under steady-state conditions, linagliptin exposure in patients with mild renal impairment was comparable to healthy subjects.

In patients with moderate renal impairment under steady-state conditions, mean exposure of linagliptin increased (AUCτ,ss by 71% and Cmax by 46%) compared with healthy subjects. This increase was not associated with a prolonged accumulation half-life, terminal half-life, or an increased accumulation factor. Renal excretion of linagliptin was below 5% of the administered dose and was not affected by decreased renal function. Patients with type 2 diabetes mellitus and severe renal impairment showed steady-state exposure approximately 40% higher than that of patients with type 2 diabetes mellitus and normal renal function (increase in AUCτ,ss by 42% and Cmax by 35%). For both type 2 diabetes mellitus groups, renal excretion was below 7% of the administered dose.

These findings were further supported by the results of population pharmacokinetic analyses.

Patients with Hepatic Impairment

GLYXAMBI: Studies characterizing the pharmacokinetics of empagliflozin and linagliptin after administration of GLYXAMBI in hepatically impaired patients have not been performed.

Empagliflozin: In patients with mild, moderate, and severe hepatic impairment according to the Child-Pugh classification, AUC of empagliflozin increased by approximately 23%, 47%, and 75% and Cmax increased by approximately 4%, 23%, and 48%, respectively, compared to subjects with normal hepatic function.

Linagliptin: In patients with mild hepatic impairment (Child-Pugh class A) steady-state exposure (AUCτ,ss) of linagliptin was approximately 25% lower and Cmax,ss was approximately 36% lower than in healthy subjects. In patients with moderate hepatic impairment (Child-Pugh class B), AUCss of linagliptin was about 14% lower and Cmax,ss was approximately 8% lower than in healthy subjects. Patients with severe hepatic impairment (Child-Pugh class C) had comparable exposure of linagliptin in terms of AUC0-24 and approximately 23% lower Cmax compared with healthy subjects. Reductions in the pharmacokinetic parameters seen in patients with hepatic impairment did not result in reductions in DPP-4 inhibition.

Drug Interaction Studies

Pharmacokinetic drug interaction studies with GLYXAMBI have not been performed; however, such studies have been conducted with the individual components of GLYXAMBI (empagliflozin and linagliptin).

Empagliflozin

In vitro Assessment of Drug Interactions

Empagliflozin does not inhibit, inactivate, or induce CYP450 isoforms. In vitro data suggest that the primary route of metabolism of empagliflozin in humans is glucuronidation by the uridine 5'-diphospho-glucuronosyltransferases UGT1A3, UGT1A8, UGT1A9 and UGT2B7. Empagliflozin does not inhibit UGT1A1, UGT1A3, UGT1A8, UGT1A9, or UGT2B7. Therefore, no effect of empagliflozin is anticipated on concomitantly administered drugs that are substrates of the major CYP450 isoforms or UGT1A1, UGT1A3, UGT1A8, UGT1A9, or UGT2B7. The effect of UGT induction (e.g., induction by rifampicin or any other UGT enzyme inducer) on empagliflozin exposure has not been evaluated.

Empagliflozin is a substrate for P-glycoprotein (P-gp) and breast cancer resistance protein (BCRP), but it does not inhibit these efflux transporters at therapeutic doses. Based on in vitro studies, empagliflozin is considered unlikely to cause interactions with drugs that are P-gp substrates. Empagliflozin is a substrate of the human uptake transporters OAT3, OATP1B1, and OATP1B3, but not OAT1 and OCT2. Empagliflozin does not inhibit any of these human uptake transporters at clinically relevant plasma concentrations and, therefore, no effect of empagliflozin is anticipated on concomitantly administered drugs that are substrates of these uptake transporters.

In vivo Assessment of Drug Interactions

Empagliflozin pharmacokinetics were similar with and without coadministration of metformin, glimepiride, pioglitazone, sitagliptin, linagliptin, warfarin, verapamil, ramipril, and simvastatin in healthy volunteers and with or without coadministration of hydrochlorothiazide and torsemide in patients with type 2 diabetes mellitus (see Figure 1). In subjects with normal renal function, coadministration of empagliflozin with probenecid resulted in a 30% decrease in the fraction of empagliflozin excreted in urine without any effect on 24-hour urinary glucose excretion. The relevance of this observation to patients with renal impairment is unknown.

Figure 1 Effect of Various Medications on the Pharmacokinetics of Empagliflozin as Displayed as 90% Confidence Interval of Geometric Mean AUC and Cmax Ratios [reference lines indicate 100% (80% - 125%)]

aempagliflozin, 50 mg, once daily; bempagliflozin, 25 mg, single dose; cempagliflozin, 25 mg, once daily; dempagliflozin, 10 mg, single dose

Empagliflozin had no clinically relevant effect on the pharmacokinetics of metformin, glimepiride, pioglitazone, sitagliptin, linagliptin, warfarin, digoxin, ramipril, simvastatin, hydrochlorothiazide, torsemide, and oral contraceptives when coadministered in healthy volunteers (see Figure 2).

Figure 2 Effect of Empagliflozin on the Pharmacokinetics of Various Medications as Displayed as 90% Confidence Interval of Geometric Mean AUC and Cmax Ratios [reference lines indicate 100% (80% - 125%)]

aempagliflozin, 50 mg, once daily; bempagliflozin, 25 mg, once daily; cempagliflozin, 25 mg, single dose; dadministered as simvastatin; eadministered as warfarin racemic mixture; fadministered as Microgynon®; gadministered as ramipril

Linagliptin

In vitro Assessment of Drug Interactions

Linagliptin is a weak to moderate inhibitor of CYP isozyme CYP3A4, but does not inhibit other CYP isozymes and is not an inducer of CYP isozymes, including CYP1A2, 2A6, 2B6, 2C8, 2C9, 2C19, 2D6, 2E1, and 4A11.

Linagliptin is a P-glycoprotein (P-gp) substrate, and inhibits P-gp mediated transport of digoxin at high concentrations. Based on these results and in vivo drug interaction studies, linagliptin is considered unlikely to cause interactions with other P-gp substrates at therapeutic concentrations.

In vivo Assessment of Drug Interactions

Strong inducers of CYP3A4 or P-gp (e.g., rifampin) decrease exposure to linagliptin to subtherapeutic and likely ineffective concentrations [see Drug Interactions (7)]. In vivo studies indicated evidence of a low propensity for causing drug interactions with substrates of CYP3A4, CYP2C9, CYP2C8, P-gp and organic cationic transporter (OCT).

Table 4 describes the effect of coadministered drugs on systemic exposure of linagliptin.

Table 4 Effect of Coadministered Drugs on Systemic Exposure of Linagliptin
Coadministered Drug | Dosing of Coadministered Druga | Dosing of Linagliptina | Geometric Mean Ratio (ratio with/without coadministered drug) No effect = 1.0
Coadministered Drug | Dosing of Coadministered Druga | Dosing of Linagliptina | AUCd | Cmax
Metformin | 850 mg TID | 10 mg QD | 1.20 | 1.03
Glyburide | 1.75 mgc | 5 mg QD | 1.02 | 1.01
Pioglitazone | 45 mg QD | 10 mg QD | 1.13 | 1.07
Ritonavir | 200 mg BID | 5 mgc | 2.01 | 2.96
Rifampinb | 600 mg QD | 5 mg QD | 0.60 | 0.56
aMultiple dose (steady-state) unless otherwise noted
bFor information regarding clinical recommendations [see Drug Interactions (7)].
cSingle dose
dAUC = AUC (0 to 24 hours) for single dose treatments and AUC = AUC (TAU) for multiple-dose treatments
QD = once daily
BID = twice daily
TID = three times daily

Table 5 describes the effect of linagliptin on systemic exposure of coadministered drugs.

Table 5 Effect of Linagliptin on Systemic Exposure of Coadministered Drugs
Coadministered Drug | Dosing of Coadministered Druga | Dosing of Linagliptina | Geometric Mean Ratio (ratio with/without coadministered drug) No effect = 1.0
Coadministered Drug | Dosing of Coadministered Druga | Dosing of Linagliptina |  | AUCc | Cmax
Metformin | 850 mg TID | 10 mg QD | metformin | 1.01 | 0.89
Glyburide | 1.75 mgb | 5 mg QD | glyburide | 0.86 | 0.86
Pioglitazone | 45 mg QD | 10 mg QD | pioglitazone | 0.94 | 0.86
Pioglitazone | 45 mg QD | 10 mg QD | metabolite M-III | 0.98 | 0.96
Pioglitazone | 45 mg QD | 10 mg QD | metabolite M-IV | 1.04 | 1.05
Digoxin | 0.25 mg QD | 5 mg QD | digoxin | 1.02 | 0.94
Simvastatin | 40 mg QD | 10 mg QD | simvastatin | 1.34 | 1.10
Simvastatin | 40 mg QD | 10 mg QD | simvastatin acid | 1.33 | 1.21
Warfarin | 10 mgb | 5 mg QD | R-warfarin | 0.99 | 1.00
Warfarin | 10 mgb | 5 mg QD | S-warfarin | 1.03 | 1.01
Warfarin | 10 mgb | 5 mg QD | INR | 0.93d | 1.04d
Warfarin | 10 mgb | 5 mg QD | PT | 1.03d | 1.15d
Ethinylestradiol and levonorgestrel | ethinylestradiol 0.03 mg and levonorgestrel 0.150 mg QD | 5 mg QD | ethinylestradiol | 1.01 | 1.08
Ethinylestradiol and levonorgestrel | ethinylestradiol 0.03 mg and levonorgestrel 0.150 mg QD | 5 mg QD | levonorgestrel | 1.09 | 1.13
aMultiple dose (steady-state) unless otherwise noted
bSingle dose
cAUC = AUC (INF) for single dose treatments and AUC = AUC (TAU) for multiple dose treatments
dAUC = AUC (0-168) and Cmax = Emax for pharmacodynamic end points
INR = International Normalized Ratio
PT = Prothrombin Time
QD = once daily
TID = three times daily

13 NONCLINICAL TOXICOLOGY

13.1 Carcinogenesis, Mutagenesis, Impairment of Fertility

GLYXAMBI

No carcinogenicity, mutagenicity, or impairment of fertility studies have been conducted with the combination of empagliflozin and linagliptin.

Empagliflozin

Carcinogenesis was evaluated in 2-year studies conducted in CD-1 mice and Wistar rats. Empagliflozin did not increase the incidence of tumors in female rats dosed at 100, 300, or 700 mg/kg/day (up to 72 times the exposure from the maximum clinical dose of 25 mg). In male rats, hemangiomas of the mesenteric lymph node were increased significantly at 700 mg/kg/day or approximately 42 times the exposure from a 25 mg clinical dose. Empagliflozin did not increase the incidence of tumors in female mice dosed at 100, 300, or 1,000 mg/kg/day (up to 62 times the exposure from a 25 mg clinical dose). Renal tubule adenomas and carcinomas were observed in male mice at 1,000 mg/kg/day, which is approximately 45 times the exposure of the maximum clinical dose of 25 mg. These tumors may be associated with a metabolic pathway predominantly present in the male mouse kidney.

Empagliflozin was not mutagenic or clastogenic with or without metabolic activation in the in vitro Ames bacterial mutagenicity assay, the in vitro L5178Y tk+/- mouse lymphoma cell assay, and an in vivo micronucleus assay in rats.

Empagliflozin had no effects on mating, fertility or early embryonic development in treated male or female rats up to the high dose of 700 mg/kg/day (approximately 155 times the 25 mg clinical dose in males and females, respectively).

Linagliptin

Linagliptin did not increase the incidence of tumors in male and female rats in a 2-year study at doses of 6, 18, and 60 mg/kg. The highest dose of 60 mg/kg is approximately 418 times the clinical dose of 5 mg/day based on AUC exposure. Linagliptin did not increase the incidence of tumors in mice in a 2-year study at doses up to 80 mg/kg (males) and 25 mg/kg (females), or approximately 35- and 270-times the clinical dose based on AUC exposure. Higher doses of linagliptin in female mice (80 mg/kg) increased the incidence of lymphoma at approximately 215-times the clinical dose based on AUC exposure.

Linagliptin was not mutagenic or clastogenic with or without metabolic activation in the Ames bacterial mutagenicity assay, a chromosomal aberration test in human lymphocytes, and an in vivo micronucleus assay.

In fertility studies in rats, linagliptin had no adverse effects on early embryonic development, mating, fertility, or bearing live young up to the highest dose of 240 mg/kg (approximately 943-times the clinical dose based on AUC exposure).

14 CLINICAL STUDIES

14.1 Glycemic Control Trials in Patients with Type 2 Diabetes Mellitus

Add-on Combination Therapy with Metformin

A total of 686 patients with type 2 diabetes mellitus participated in a double-blind, active-controlled trial to evaluate the efficacy of empagliflozin 10 mg or 25 mg in combination with linagliptin 5 mg compared to the individual components.

Patients with type 2 diabetes mellitus inadequately controlled on at least 1,500 mg of metformin per day entered a single-blind placebo run-in period for 2 weeks. At the end of the run-in period, patients who remained inadequately controlled and had an HbA1c between 7% and 10.5% were randomized 1:1:1:1:1 to one of 5 active-treatment arms of empagliflozin 10 mg or 25 mg, linagliptin 5 mg, or linagliptin 5 mg in combination with 10 mg or 25 mg empagliflozin as a fixed dosage combination tablet.

At Week 24, empagliflozin 10 mg or 25 mg used in combination with linagliptin 5 mg provided statistically significant improvement in HbA1c (p-value <0.0001) and FPG (p-value <0.001) compared to the individual components in patients who had been inadequately controlled on metformin (see Table 6, Figure 3). Treatment with GLYXAMBI 25 mg/5 mg or GLYXAMBI 10 mg/5 mg daily also resulted in a statistically significant reduction in body weight compared to linagliptin 5 mg (p-value <0.0001). There was no statistically significant difference compared to empagliflozin alone.

Table 6 Glycemic Parameters at 24 Weeks in a Trial Comparing GLYXAMBI to the Individual Components as Add-on Therapy in Patients Inadequately Controlled on Metformin
 | GLYXAMBI 10 mg/5 mg | GLYXAMBI 25 mg/5 mg | Empagliflozin 10 mg | Empagliflozin 25 mg | Linagliptin 5 mg
HbA1c (%)
Number of patients | n=135 | n=133 | n=137 | n=139 | n=128
Baseline (mean) | 8.0 | 7.9 | 8.0 | 8.0 | 8.0
Change from baseline (adjusted mean) | -1.1 | -1.2 | -0.7 | -0.6 | -0.7
Comparison vs empagliflozin 25 mg or 10 mg (adjusted mean) (95% CI)a | -0.4 (-0.6, -0.2)d | -0.6 (-0.7, -0.4)d | -- | -- | --
Comparison vs linagliptin 5 mg (adjusted mean) (95% CI)a | -0.4 (-0.6, -0.2)d | -0.5 (-0.7, -0.3)d | -- | -- | --
Patients [n (%)] achieving HbA1c <7%b | 74 (58) | 76 (62) | 35 (28) | 43 (33) | 43 (36)
FPG (mg/dL)
Number of patients | n=133 | n=131 | n=136 | n=137 | n=125
Baseline (mean) | 157 | 155 | 162 | 160 | 156
Change from baseline (adjusted mean) | -33 | -36 | -21 | -21 | -13
Comparison vs empagliflozin 25 mg or 10 mg (adjusted mean) (95% CI)a | -12 (-18, -5)d | -15 (-22, -9)d | -- | -- | --
Comparison vs linagliptin 5 mg (adjusted mean) (95% CI)a | -20 (-27, -13)d | -23 (-29, -16)d | -- | -- | --
Body Weight
Number of patients | n=135 | n=134 | n=137 | n=140 | n=128
Baseline (mean) in kg | 87 | 85 | 86 | 88 | 85
% change from baseline (adjusted mean) | -3.1 | -3.4 | -3.0 | -3.5 | -0.7
Comparison vs empagliflozin 25 mg or 10 mg (adjusted mean) (95% CI)c | 0.0 (-0.9, 0.8) | 0.1 (-0.8, 0.9) | -- | -- | --
Comparison vs linagliptin 5 mg (adjusted mean) (95% CI)c | -2.4 (-3.3, -1.5)d | -2.7 (-3.6, -1.8)d | -- | -- | --
aFull analysis population (observed case) using MMRM. MMRM model included treatment, renal function, region, visit, visit by treatment interaction, and baseline HbA1c.
bPatients with HbA1c above 7% at baseline: GLYXAMBI 25 mg/5 mg, n=123; GLYXAMBI 10 mg/5 mg, n=128; empagliflozin 25 mg, n=132; empagliflozin 10 mg, n=125; linagliptin 5 mg, n=119. Non-completers were considered failures (NCF).
cFull analysis population using last observation carried forward. ANCOVA model included treatment, renal function, region, baseline weight, and baseline HbA1c.
dp<0.001 for FPG; p<0.0001 for HbA1c and body weight

Figure 3 Adjusted Mean HbA1c Change at Each Time Point (Completers) and at Week 24 (mITT population)

14.2 Empagliflozin Cardiovascular Outcomes in Patients with Type 2 Diabetes Mellitus and Atherosclerotic Cardiovascular Disease

EMPA-REG OUTCOME was a multicenter, multinational, randomized, double-blind parallel group trial that compared the risk of experiencing a major adverse cardiovascular event (MACE) between empagliflozin and placebo when these were added to and used concomitantly with standard of care treatments for diabetes mellitus and atherosclerotic CV disease. Concomitant antidiabetic medications were kept stable for the first 12 weeks of the trial. Thereafter, antidiabetic and atherosclerotic therapies could be adjusted, at the discretion of investigators, to ensure participants were treated according to the standard care for these diseases.

A total of 7,020 patients were treated (empagliflozin 10 mg = 2,345; empagliflozin 25 mg = 2,342; placebo = 2,333) and followed for a median of 3.1 years. Approximately 72% of the trial population was White, 22% was Asian, and 5% was Black or African American. The mean age was 63 years and approximately 72% were male.

All patients in the trial had inadequately controlled type 2 diabetes mellitus at baseline (HbA1c greater than or equal to 7%). The mean HbA1c at baseline was 8.1% and 57% of participants had diabetes mellitus for more than 10 years. Approximately 31%, 22% and 20% reported a past history of neuropathy, retinopathy and nephropathy to investigators, respectively and the mean eGFR was 74 mL/min/1.73 m^2. At baseline, patients were treated with one (~30%) or more (~70%) antidiabetic medications including metformin (74%), insulin (48%), sulfonylurea (43%) and dipeptidyl peptidase-4 inhibitor (11%).

All patients had established atherosclerotic CV disease at baseline including one (82%) or more (18%) of the following: a documented history of coronary artery disease (76%), stroke (23%) or peripheral artery disease (21%). At baseline, the mean systolic blood pressure was 136 mmHg, the mean diastolic blood pressure was 76 mmHg, the mean LDL was 86 mg/dL, the mean HDL was 44 mg/dL, and the mean urinary albumin to creatinine ratio (UACR) was 175 mg/g. At baseline, approximately 81% of patients were treated with renin angiotensin system inhibitors, 65% with beta-blockers, 43% with diuretics, 77% with statins, and 86% with antiplatelet agents (mostly aspirin).

The primary endpoint in EMPA-REG OUTCOME was the time to first occurrence of a Major Adverse Cardiac Event (MACE). A major adverse cardiac event was defined as occurrence of either a CV death or a non-fatal myocardial infarction (MI) or a non-fatal stroke. The statistical analysis plan had pre-specified that the 10 and 25 mg dosages would be combined. A Cox proportional hazards model was used to test for non-inferiority against the pre-specified risk margin of 1.3 for the hazard ratio of MACE and superiority on MACE if non-inferiority was demonstrated. Type-1 error was controlled across multiples tests using a hierarchical testing strategy.

Empagliflozin significantly reduced the risk of first occurrence of primary composite endpoint of CV death, non-fatal myocardial infarction, or non-fatal stroke (HR: 0.86; 95% CI: 0.74, 0.99). The treatment effect was due to a significant reduction in the risk of CV death in subjects randomized to empagliflozin (HR: 0.62; 95% CI: 0.49, 0.77), with no change in the risk of non-fatal myocardial infarction or non-fatal stroke (see Table 7 and Figures 4 and 5). Results for the 10 mg and 25 mg empagliflozin dosages were consistent with results for the combined dosage groups.

Table 7 Treatment Effect for the Primary Composite Endpoint and its Componentsa
 | Placebo N=2,333 | Empagliflozin N=4,687 | Hazard ratio vs placebo (95% CI)
Composite of CV death, non-fatal myocardial infarction, non-fatal stroke (time to first occurrence)b | 282 (12.1%) | 490 (10.5%) | 0.86 (0.74, 0.99)
Non-fatal myocardial infarctionc | 121 (5.2%) | 213 (4.5%) | 0.87 (0.70, 1.09)
Non-fatal strokec | 60 (2.6%) | 150 (3.2%) | 1.24 (0.92, 1.67)
CV deathc | 137 (5.9%) | 172 (3.7%) | 0.62 (0.49, 0.77)
aTreated set (patients who had received at least one dose of trial drug)
bp-value for superiority (2-sided) 0.04
cTotal number of events

Figure 4 Estimated Cumulative Incidence of First MACE

Figure 5 Estimated Cumulative Incidence of CV Death

The efficacy of empagliflozin on CV death was generally consistent across major demographic and disease subgroups.

Vital status was obtained for 99.2% of subjects in the trial. A total of 463 deaths were recorded during the EMPA-REG OUTCOME trial. Most of these deaths were categorized as CV deaths. The non-CV deaths were only a small proportion of deaths and were balanced between the treatment groups (2.1% in patients treated with empagliflozin, and 2.4% of patients treated with placebo).

14.3 Linagliptin Cardiovascular Safety Trials in Patients with Type 2 Diabetes Mellitus

CARMELINA

The CV risk of linagliptin was evaluated in CARMELINA, a multinational, multi-center, placebo-controlled, double-blind, parallel group trial comparing linagliptin (N=3,494) to placebo (N=3,485) in adult patients with type 2 diabetes mellitus and a history of established macrovascular and/or renal disease. The trial compared the risk of major adverse cardiovascular events (MACE) between linagliptin and placebo when these were added to standard of care treatments for diabetes mellitus and other CV risk factors. The trial was event driven, the median duration of follow-up was 2.2 years and vital status was obtained for 99.7% of patients.

Patients were eligible to enter the trial if they were adults with type 2 diabetes mellitus, with HbA1c of 6.5% to 10%, and had either albuminuria and previous macrovascular disease (39% of enrolled population), or evidence of impaired renal function by eGFR and Urinary Albumin Creatinine Ratio (UACR) criteria (42% of enrolled population), or both (18% of enrolled population).

At baseline the mean age was 66 years and the population was 63% male, 80% White, 9% Asian, 6% Black or African American and 36% were of Hispanic or Latino ethnicity. Mean HbA1c was 8.0% and mean duration of type 2 diabetes mellitus was 15 years. The trial population included 17% patients ≥75 years of age and 62% patients with renal impairment defined as eGFR <60 mL/min/1.73 m^2. The mean eGFR was 55 mL/min/1.73 m^2 and 27% of patients had mild renal impairment (eGFR 60 to 90 mL/min/1.73 m^2), 47% of patients had moderate renal impairment (eGFR 30 to <60 mL/min/1.73 m^2) and 15% of patients had severe renal impairment (eGFR <30 mL/min/1.73 m^2). Patients were taking at least one antidiabetic drug (97%), and the most common were insulin and analogues (57%), metformin (54%) and sulfonylurea (32%). Patients were also taking antihypertensives (96%), lipid lowering drugs (76%) with 72% on statin, and aspirin (62%).

The primary endpoint, MACE, was the time to first occurrence of one of three composite outcomes which included CV death, non-fatal myocardial infarction or non-fatal stroke. The trial was designed as a non-inferiority trial with a pre-specified risk margin of 1.3 for the hazard ratio of MACE. A total of 434 patients on linagliptin and 420 patients on placebo experienced MACE. The incidence rate of MACE in both treatment arms: 56.3 MACE per 1,000 patient-years on placebo vs. 57.7 MACE per 1,000 patient-years on linagliptin. The estimated hazard ratio for MACE associated with linagliptin relative to placebo was 1.02 with a 95% confidence interval of (0.89, 1.17). The upper bound of this confidence interval, 1.17, excluded the risk margin of 1.3.

CAROLINA

The CV risk of linagliptin was evaluated in CAROLINA, a multi-center, multinational, randomized, double-blind parallel group trial comparing linagliptin (N=3,023) to glimepiride (N=3,010) in adult patients with type 2 diabetes mellitus and a history of established CV disease and/or multiple CV risk factors. The trial compared the risk of major adverse cardiovascular events (MACE) between linagliptin and glimepiride when these were added to standard of care treatments for diabetes mellitus and other CV risk factors. The trial was event driven, the median duration of follow-up was 6.23 years and vital status was obtained for 99.3% of patients.

Patients were eligible to enter the trial if they were adults with type 2 diabetes mellitus with insufficient glycemic control (defined as HbA1c of 6.5% to 8.5% or 6.5% to 7.5% depending on treatment-naïve, on monotherapy or on combination therapy), and were defined to be at high CV risk with previous vascular disease, evidence of vascular related end-organ damage, age ≥70 years, and/or two CV risk factors (duration of diabetes mellitus >10 years, systolic blood pressure >140 mmHg, current smoker, LDL cholesterol ≥135 mg/dL).

At baseline the mean age was 64 years and the population was 60% male, 73% White, 18% Asian, 5% Black or African American, and 17% were of Hispanic or Latino ethnicity. The mean HbA1c was 7.15% and mean duration of type 2 diabetes mellitus was 7.6 years. The trial population included 34% patients ≥70 years of age and 19% patients with renal impairment defined as eGFR <60 mL/min/1.73 m^2. The mean eGFR was 77 mL/min/1.73 m^2. Patients were taking at least one antidiabetic drug (91%) and the most common were metformin (83%) and sulfonylurea (28%). Patients were also taking antihypertensives (89%), lipid lowering drugs (70%) with 65% on statin, and aspirin (47%).

The primary endpoint, MACE, was the time to first occurrence of one of three composite outcomes which included CV death, non-fatal myocardial infarction or non-fatal stroke. The trial was designed as a non-inferiority trial with a pre-specified risk margin of 1.3 for the hazard ratio of MACE. A total of 356 patients on linagliptin and 362 patients on glimepiride experienced MACE. The incidence rate of MACE in both treatment arms: 20.7 MACE per 1,000 patient-years on linagliptin vs. 21.2 MACE per 1,000 patient-years on glimepiride. The estimated hazard ratio for MACE associated with linagliptin relative to glimepiride was 0.98 with a 95% confidence interval of (0.84, 1.14). The upper bound of this confidence interval, 1.14, excluded the risk margin of 1.3.

16 HOW SUPPLIED/STORAGE AND HANDLING

GLYXAMBI tablets are available as follows:

10 mg/5 mg tablets: pale yellow, arc triangular, flat-faced, bevel-edged, film-coated tablets. One side is debossed with the Boehringer Ingelheim company symbol; the other side is debossed with "10/5".

Bottles of 30 (NDC 0597-0182-30)
Bottles of 90 (NDC 0597-0182-90)
Cartons containing 3 blister cards of 10 tablets each (3 × 10) (NDC 0597-0182-39), institutional pack.

25 mg/5 mg tablets: pale pink, arc triangular, flat-faced, bevel-edged, film-coated tablets. One side is debossed with the Boehringer Ingelheim company symbol; the other side is debossed with "25/5".

Bottles of 30 (NDC 0597-0164-30)
Bottles of 90 (NDC 0597-0164-90)
Cartons containing 3 blister cards of 10 tablets each (3 × 10) (NDC 0597-0164-39), institutional pack.

If repackaging is required, dispense in a tight container as defined in USP.

Storage

Store at 20°C to 25°C (68°F to 77°F); excursions permitted to 15°C to 30°C (59°F to 86°F) [see USP Controlled Room Temperature].

17 PATIENT COUNSELING INFORMATION

Advise the patient to read the FDA-approved patient labeling (Medication Guide).

Diabetic Ketoacidosis in Patients with Type 1 Diabetes Mellitus and Other Ketoacidosis

Inform patients that GLYXAMBI can cause potentially fatal ketoacidosis and that type 2 diabetes mellitus and pancreatic disorders (e.g., history of pancreatitis or pancreatic surgery) are risk factors.

Educate all patients on precipitating factors (such as insulin dose reduction or missed insulin doses, infection, reduced caloric intake, ketogenic diet, surgery, dehydration, and alcohol abuse) and symptoms of ketoacidosis (including nausea, vomiting, abdominal pain, tiredness, and labored breathing). Inform patients that blood glucose may be normal even in the presence of ketoacidosis.

Advise patients that they may be asked to monitor ketones. If symptoms of ketoacidosis occur, instruct patients to discontinue GLYXAMBI and seek medical attention immediately [see Warnings and Precautions (5.1)].

Pancreatitis

Inform patients that acute pancreatitis has been reported during use of linagliptin. Inform patients that persistent severe abdominal pain, sometimes radiating to the back, which may or may not be accompanied by vomiting, is the hallmark symptom of acute pancreatitis. Instruct patients to discontinue GLYXAMBI promptly and contact their healthcare provider if persistent severe abdominal pain occurs [see Warnings and Precautions (5.2)].

Volume Depletion

Inform patients that symptomatic hypotension may occur with GLYXAMBI and advise them to contact their healthcare provider if they experience such symptoms [see Warnings and Precautions (5.3)]. Inform patients that dehydration may increase the risk for hypotension, and to maintain adequate fluid intake.

Genitourinary Infections, including Urosepsis, Pyelonephritis, Necrotizing Fasciitis of the Perineum (Fournier's Gangrene), and Genital Mycotic Infections

Counsel patients that genitourinary infections may occur when taking empagliflozin, a component of GLYXAMBI, and may become serious. Educate them on the symptoms and advise them to seek medical advice if symptoms occur. Specifically, advise patients to promptly seek medical attention if they develop pain or tenderness, redness, or swelling of the genitals or the area from the genitals back to the rectum, along with a fever above 100.4°F or malaise [see Warnings and Precautions (5.4)].

Hypoglycemia with Concomitant Use with Insulin and Insulin Secretagogues

Inform patients that the risk of hypoglycemia is increased when GLYXAMBI is used in combination with an insulin secretagogue (e.g., sulfonylurea) or insulin [see Warnings and Precautions (5.5)].

Lower Limb Amputation

Counsel patients about the importance of routine preventative foot care. Instruct patients to monitor for new pain or tenderness, sores or ulcers, or infections involving the leg or foot and to seek medical advice immediately if such signs or symptoms develop [see Warnings and Precautions (5.6)].

Hypersensitivity Reactions

Inform patients that serious allergic reactions, such as anaphylaxis, angioedema, and exfoliative skin conditions, have been reported during postmarketing use of linagliptin or empagliflozin, components of GLYXAMBI. If symptoms of allergic reactions (such as rash, skin flaking or peeling, urticaria, swelling of the skin, or swelling of the face, lips, tongue, and throat that may cause difficulty in breathing or swallowing) occur, patients must stop taking GLYXAMBI and seek medical advice promptly [see Warnings and Precautions (5.7)].

Severe and Disabling Arthralgia

Inform patients that severe and disabling joint pain may occur with this class of drugs. The time to onset of symptoms can range from one day to years. Instruct patients to seek medical advice if severe joint pain occurs [see Warnings and Precautions (5.8)].

Bullous Pemphigoid

Inform patients that bullous pemphigoid has been reported during use of linagliptin. Instruct patients to seek medical advice if blisters or erosions occur [see Warnings and Precautions (5.9)].

Heart Failure

Inform patients of the signs and symptoms of heart failure. Before initiating GLYXAMBI, patients should be asked about a history of heart failure or other risk factors for heart failure including moderate to severe renal impairment. Instruct patients to contact their healthcare provider as soon as possible if they experience symptoms of heart failure, including increasing shortness of breath, rapid increase in weight or swelling of the feet [see Warnings and Precautions (5.10)].

Laboratory Tests

Inform patients that elevated glucose in urinalysis is expected when taking GLYXAMBI [see Drug Interactions (7)].

Pregnancy

Advise pregnant patients, and patients of reproductive potential, of the potential risk to a fetus with treatment with GLYXAMBI [see Use in Specific Populations (8.1)]. Instruct patients to report pregnancies to their healthcare provider as soon as possible.

Lactation

Advise patients that breastfeeding is not recommended during treatment with GLYXAMBI [see Use in Specific Populations (8.2)].

Missed Dose

Instruct patients to take GLYXAMBI only as prescribed. If a dose is missed, it should be taken as soon as the patient remembers. Advise patients not to double their next dose [see Dosage and Administration (2.5)].

Distributed by:
Boehringer Ingelheim Pharmaceuticals, Inc.
Ridgefield, CT 06877 USA

Licensed from:
Boehringer Ingelheim International GmbH, Ingelheim, Germany.

GLYXAMBI is a registered trademark of and used under license from Boehringer Ingelheim International GmbH.

Boehringer Ingelheim Pharmaceuticals, Inc. either owns or uses the Jardiance®, Tradjenta®, EMPA-REG OUTCOME®, CARMELINA®, and CAROLINA® trademarks under license.

The other brands listed are trademarks of their respective owners and are not trademarks of Boehringer Ingelheim Pharmaceuticals, Inc.

Copyright © 2026 Boehringer Ingelheim International GmbH
ALL RIGHTS RESERVED

COL8994JA062026
SPL8995J

MEDICATION GUIDE
GLYXAMBI® (glik-SAM-bee)
(empagliflozin and linagliptin tablets)
for oral use

What is the most important information I should know about GLYXAMBI?
GLYXAMBI can cause serious side effects, including:

- Diabetic ketoacidosis (increased ketones in your blood or urine) in people with type 1 and other ketoacidosis. GLYXAMBI can cause ketoacidosis that can be life-threatening and may lead to death. Ketoacidosis is a serious condition which needs to be treated in a hospital. People with type 1 diabetes have a high risk of getting ketoacidosis. People with type 2 diabetes or pancreas problems also have an increased risk of getting ketoacidosis. Ketoacidosis can also happen in people who: are sick, cannot eat or drink as usual, skip meals, are on a diet high in fat and low in carbohydrates (ketogenic diet), take less than the usual amount of insulin or miss insulin doses, drink too much alcohol, have a loss of too much fluid from the body (volume depletion), or who have surgery. Ketoacidosis can happen even if your blood sugar is less than 250 mg/dL. Your healthcare provider may ask you to periodically check ketones in your urine or blood.
  Stop taking GLYXAMBI and call your healthcare provider or get medical help right away if you get any of the following. If possible, check for ketones in your urine or blood, even if your blood sugar is less than 250 mg/dL:

- nausea
- vomiting
- stomach-area (abdominal) pain

- tiredness
- trouble breathing
- ketones in your urine or blood

- Inflammation of the pancreas (pancreatitis) which may be severe and lead to death. Certain medical problems make you more likely to get pancreatitis.
  Before you start taking GLYXAMBI, tell your healthcare provider if you have ever had:

- inflammation of your pancreas (pancreatitis)
- a history of alcoholism

- stones in your gallbladder (gallstones)
- high blood triglyceride levels

Stop taking GLYXAMBI and call your healthcare provider right away if you have pain in your stomach area (abdomen) that is severe and will not go away. The pain may be felt going from your abdomen to your back. The pain may happen with or without vomiting. These may be symptoms of pancreatitis.

- Dehydration. GLYXAMBI can cause some people to become dehydrated (the loss of body water and salt). Dehydration may cause you to feel dizzy, faint, light-headed, or weak, especially when you stand up (orthostatic hypotension). There have been reports of sudden worsening of kidney function in people who are taking GLYXAMBI. You may be at higher risk of dehydration if you:
  - take medicines to lower your blood pressure, including diuretics (water pills)
  - are on a low sodium (salt) diet
  - have kidney problems
  - are 65 years of age or older
  Talk to your healthcare provider about what you can do to prevent dehydration including how much fluid you should drink on a daily basis. Call your healthcare provider right away if you reduce the amount of food or liquid you drink, for example if you are sick or you cannot eat, or start to lose liquids from your body, for example from vomiting, diarrhea or being in the sun too long.

What is GLYXAMBI?

GLYXAMBI is a prescription medicine that contains 2 diabetes medicines, empagliflozin (JARDIANCE) and linagliptin (TRADJENTA). GLYXAMBI can be used:

- along with diet and exercise to lower blood sugar (glucose) in adults with type 2 diabetes,
- in adults with type 2 diabetes who have known cardiovascular disease when empagliflozin (JARDIANCE), one of the medicines in GLYXAMBI, is needed to reduce the risk of cardiovascular death.

- GLYXAMBI is not for use to lower blood sugar (glucose) in people with type 1 diabetes. It may increase their risk of diabetic ketoacidosis (increased ketones in blood or urine).
- If you have had pancreatitis in the past, it is not known if you have a higher chance of getting pancreatitis while you take GLYXAMBI.
- GLYXAMBI is not for use to lower blood sugar (glucose) in people with type 2 diabetes who have severe kidney problems, because it may not work.
- It is not known if GLYXAMBI is safe and effective in children.

Who should not take GLYXAMBI?
Do not take GLYXAMBI if you:

- are allergic to linagliptin (TRADJENTA), empagliflozin (JARDIANCE) or any of the ingredients in GLYXAMBI. See the end of this Medication Guide for a complete list of ingredients in GLYXAMBI.
  Symptoms of a serious allergic reaction to GLYXAMBI may include:
  - skin rash, itching, flaking or peeling
  - raised red patches on your skin (hives)
  - swelling of your face, lips, tongue and throat that may cause difficulty in breathing or swallowing
  - difficulty with swallowing or breathing

If you have any of these symptoms, stop taking GLYXAMBI and call your healthcare provider right away or go to the nearest hospital emergency room.

What should I tell my healthcare provider before taking GLYXAMBI?
Before taking GLYXAMBI, tell your healthcare provider about all of your medical conditions, including if you:

- have type 1 diabetes or have had diabetic ketoacidosis.
- have a decrease in your insulin dose.
- have a serious infection.
- have a history of infection of the vagina or penis.
- have a history of amputation.
- have kidney problems.
- have liver problems.
- have a history of urinary tract infections or problems with urination.
- are on a low sodium (salt) diet. Your healthcare provider may change your diet or your dose.
- are going to have surgery. Your healthcare provider may stop your GLYXAMBI before you have surgery. Talk to your healthcare provider if you are having surgery about when to stop taking GLYXAMBI and when to start it again.
- are eating less, or there is a change in your diet.
- are dehydrated.
- have or have had problems with your pancreas, including pancreatitis or surgery on your pancreas.
- drink alcohol very often, or drink a lot of alcohol in the short term ("binge" drinking).
- have ever had an allergic reaction to GLYXAMBI.
- are pregnant or plan to become pregnant. GLYXAMBI may harm your unborn baby. If you become pregnant while taking GLYXAMBI, tell your healthcare provider as soon as possible. Talk with your healthcare provider about the best way to control your blood sugar while you are pregnant.
- are breastfeeding or plan to breastfeed. GLYXAMBI may pass into your breast milk and may harm your baby. Talk with your healthcare provider about the best way to feed your baby if you are taking GLYXAMBI. Do not breastfeed while taking GLYXAMBI.

Tell your healthcare provider about all the medicines you take, including prescription and over-the-counter medicines, vitamins, and herbal supplements.
GLYXAMBI may affect the way other medicines work, and other medicines may affect how GLYXAMBI works.
Know the medicines you take. Keep a list of them to show your healthcare provider and pharmacist when you get a new medicine.

How should I take GLYXAMBI?

- Take GLYXAMBI exactly as your healthcare provider tells you to take it.
- Take GLYXAMBI by mouth 1 time each day in the morning, with or without food.
- Your healthcare provider will tell you how much GLYXAMBI to take and when to take it. Your healthcare provider may change your dose if needed.
- Your healthcare provider may tell you to take GLYXAMBI along with other diabetes medicines. Low blood sugar can happen more often when GLYXAMBI is taken with certain other diabetes medicines. See "What are the possible side effects of GLYXAMBI?"
- If you miss a dose, take it as soon as you remember. If it is almost time for your next dose, skip the missed dose and take the medicine at the next regularly scheduled time. Do not take two doses of GLYXAMBI at the same time. Talk with your healthcare provider if you have questions about a missed dose.
- If you take too much GLYXAMBI, call your healthcare provider or Poison Help line at 1-800-222-1222, or go to the nearest hospital emergency room right away.
- When taking GLYXAMBI, you may have sugar in your urine, which will show up on a urine test.
- When your body is under some types of stress, such as fever, trauma (such as a car accident), infection, or surgery, the amount of diabetes medicine you need may change. Tell your healthcare provider right away if you have any of these conditions and follow your healthcare provider's instructions.
- Your healthcare provider may do certain blood tests before you start GLYXAMBI and during treatment as needed.

What are the possible side effects of GLYXAMBI?
GLYXAMBI may cause serious side effects, including:

- See "What is the most important information I should know about GLYXAMBI?"
- Genital and urinary tract infections. Empagliflozin, one of the medicines in GLYXAMBI, can cause serious infections in your genital area or urinary tract that could require hospitalization. A rare but serious bacterial infection called necrotizing fasciitis can cause damage to the tissue under the skin in the area between and around the anus and genitals (perineum). This infection may require hospitalization, multiple surgeries, and could lead to death. Seek medical attention immediately if you have a fever or you are feeling very weak, tired or uncomfortable (malaise), and you develop any of the following symptoms in the area between and around your anus and genitals:

- pain or tenderness

- swelling

- redness of skin (erythema)

Also tell your healthcare provider if you have any of these signs or symptoms of urinary tract infections or yeast infections:

- Urinary tract infection:
  - burning feeling when you urinate
  - need to urinate often or right away
  - pain in the lower part of your stomach (pelvis)
  - blood in your urine
  You may also have a fever, back pain, nausea, or vomiting.
- Vaginal yeast infection:
  - vaginal odor
  - white or yellowish vaginal discharge (may be lumpy or look like cottage cheese)
  - vaginal itching
- Yeast infection of the skin around the penis (balanitis or balanoposthitis): If you are uncircumcised, swelling may make it difficult to pull back the skin around the tip of your penis. Other symptoms include:

- redness, itching, or swelling of the penis
- bad smelling discharge from the penis

- rash on the penis
- pain in the skin around the penis

Talk to your healthcare provider about what to do if you get symptoms of a yeast infection. They may suggest you use an over-the-counter antifungal medicine. Contact your healthcare provider right away if your symptoms do not improve after using an over-the-counter antifungal medicine.

- Low blood sugar (hypoglycemia). If you take GLYXAMBI with another medicine that can cause low blood sugar, such as a sulfonylurea or insulin, your risk of getting low blood sugar is higher. The dose of your sulfonylurea medicine or insulin may need to be lowered while you take GLYXAMBI. Signs and symptoms of low blood sugar may include:

- headache
- drowsiness
- weakness

- irritability
- hunger
- fast heartbeat

- confusion
- shaking or feeling jittery

- dizziness
- sweating

- Amputations. SGLT2 inhibitors may increase your risk of lower limb amputations.
  You may be at a higher risk of lower limb amputation if you:
  - have a history of amputation
  - have had blocked or narrowed blood vessels, usually in your leg
  - have had diabetic foot infection, ulcers or sores
  Call your healthcare provider right away if you have new pain or tenderness, any sores, ulcers, or infections in your leg or foot. Talk to your healthcare provider about proper foot care.
- Serious allergic reactions. If you have any symptoms of a serious allergic reaction, stop taking GLYXAMBI and call your healthcare provider right away or go to the nearest hospital emergency room. See "Who should not take GLYXAMBI?".
- Joint pain. Some people who take linagliptin, one of the medicines in GLYXAMBI, may develop joint pain that can be severe. Call your healthcare provider if you have severe joint pain.
- Skin reaction. Some people who take medicines called DPP-4 inhibitors, one of the medicines in GLYXAMBI, may develop a skin reaction called bullous pemphigoid that can require treatment in a hospital. Tell your healthcare provider right away if you develop blisters or the breakdown of the outer layer of your skin (erosion). Your healthcare provider may tell you to stop taking GLYXAMBI.
- Heart failure. Heart failure means your heart does not pump blood well enough.
  Before you start taking GLYXAMBI, tell your healthcare provider if you have ever had heart failure or have problems with your kidneys. Contact your healthcare provider right away if you have any of the following symptoms:
  - increasing shortness of breath or trouble breathing, especially when you lie down
  - swelling or fluid retention, especially in the feet, ankles or legs
  - an unusually fast increase in weight
  - unusual tiredness
  These may be symptoms of heart failure.

The most common side effects of GLYXAMBI include:

- urinary tract infection
- upper respiratory tract infection

- stuffy or runny nose and sore throat

Tell your healthcare provider if you have any side effect that bothers you or that does not go away.
These are not all the possible side effects of GLYXAMBI. For more information, ask your healthcare provider or pharmacist.
Call your doctor for medical advice about side effects. You may report side effects to FDA at 1-800-FDA-1088.

How should I store GLYXAMBI?

- Store GLYXAMBI at room temperature between 68°F to 77°F (20°C to 25°C).
- Keep GLYXAMBI and all medicines out of the reach of children.

General information about the safe and effective use of GLYXAMBI.
Medicines are sometimes prescribed for purposes other than those listed in a Medication Guide. Do not use GLYXAMBI for a condition for which it was not prescribed. Do not give GLYXAMBI to other people, even if they have the same symptoms that you have. It may harm them.
You can ask your pharmacist or healthcare provider for information about GLYXAMBI that is written for health professionals.

What are the ingredients in GLYXAMBI?
Active ingredients: empagliflozin and linagliptin
Inactive ingredients: copovidone, corn starch, crospovidone, magnesium stearate, mannitol, pregelatinized starch, and talc. The film coating contains the following inactive ingredients: hypromellose, mannitol, polyethylene glycol, talc, and titanium dioxide.
10 mg/5 mg tablets also contain ferric oxide yellow.
25 mg/5 mg tablets also contain ferric oxide red.

Distributed by: Boehringer Ingelheim Pharmaceuticals, Inc., Ridgefield, CT 06877 USA
Licensed from: Boehringer Ingelheim International GmbH, Ingelheim, Germany
GLYXAMBI is a registered trademark of and used under license from Boehringer Ingelheim International GmbH.
Boehringer Ingelheim Pharmaceuticals, Inc. either owns or uses the Jardiance®, Tradjenta®, EMPA-REG OUTCOME®, CARMELINA®, and CAROLINA® trademarks under license.
The other brands listed are trademarks of their respective owners and are not trademarks of Boehringer Ingelheim Pharmaceuticals, Inc.
Copyright © 2026 Boehringer Ingelheim International GmbH
ALL RIGHTS RESERVED
COL8994JA062026
For more information about GLYXAMBI, including current prescribing information and Medication Guide, go to www.glyxambi.com, scan the code, or call Boehringer Ingelheim Pharmaceuticals, Inc. at 1-800-542-6257.

This Medication Guide has been approved by the U.S. Food and Drug Administration.

Revised: January 2026

PRINCIPAL DISPLAY PANEL - 10 mg/5 mg Tablet Bottle Label

NDC 0597-0182-90

Glyxambi®

(empagliflozin and
linagliptin tablets)

10 mg/5 mg

DISPENSE WITH ACCOMPANYING MEDICATION GUIDE

90 tablets
Rx only

Boehringer
Ingelheim

PRINCIPAL DISPLAY PANEL - 25 mg/5 mg Tablet Bottle Label

NDC 0597-0164-90

Glyxambi®

(empagliflozin and
linagliptin tablets)

25 mg/5 mg

DISPENSE WITH ACCOMPANYING MEDICATION GUIDE

90 tablets
Rx only

Boehringer
Ingelheim